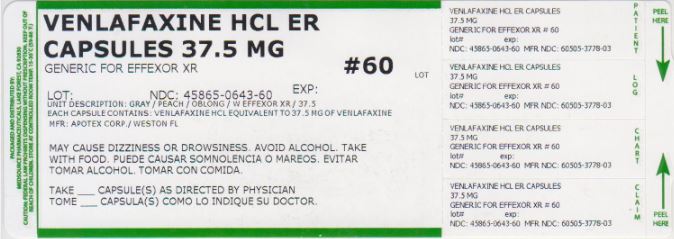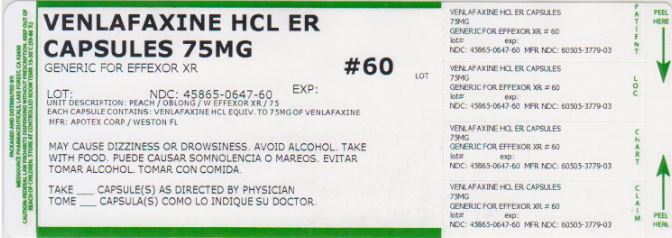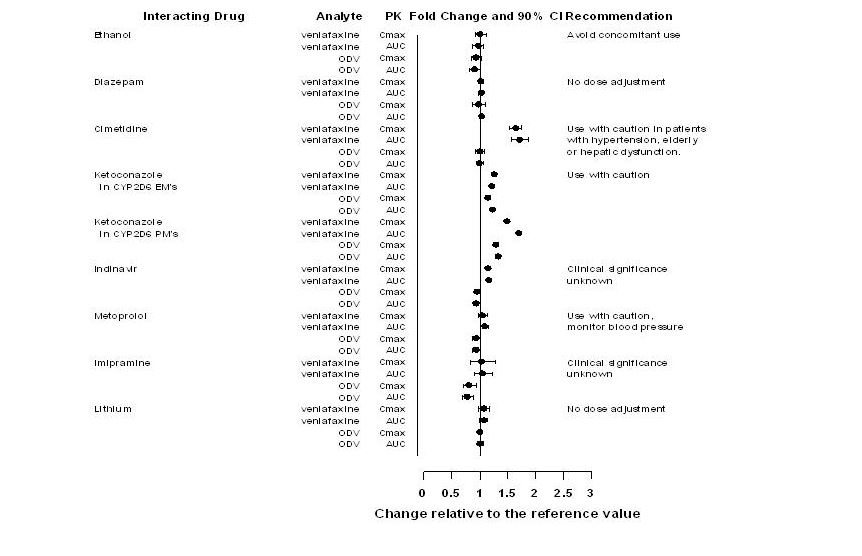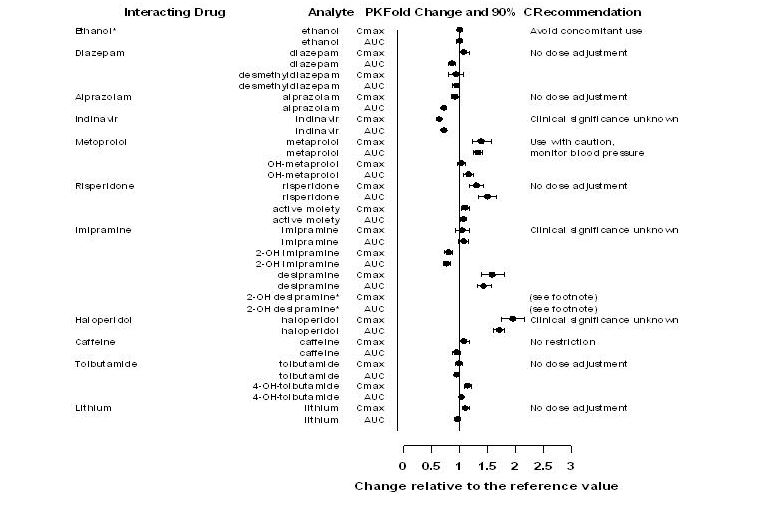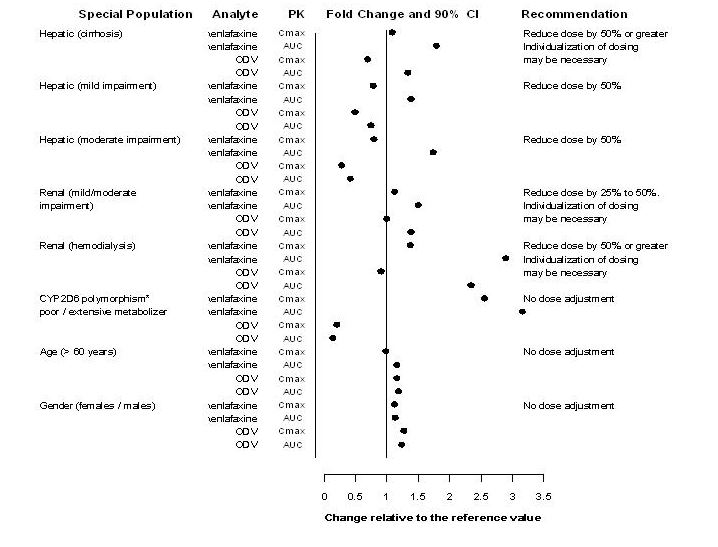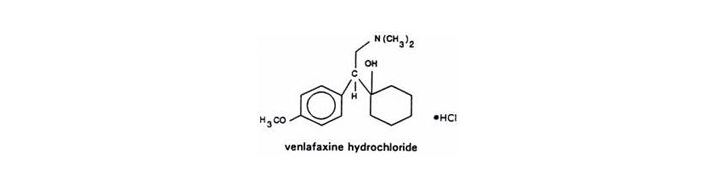 DRUG LABEL: Venlafaxine Hydrochloride
NDC: 45865-643 | Form: CAPSULE, EXTENDED RELEASE
Manufacturer: Medsource Pharmaceuticals
Category: prescription | Type: HUMAN PRESCRIPTION DRUG LABEL
Date: 20191227

ACTIVE INGREDIENTS: VENLAFAXINE HYDROCHLORIDE 37.5 mg/1 1
INACTIVE INGREDIENTS: POWDERED CELLULOSE; GELATIN; FERRIC OXIDE RED; TITANIUM DIOXIDE; HYPROMELLOSES; ETHYLCELLULOSE (100 MPA.S); HYPROMELLOSE 2910 (6 MPA.S)

HIGHLIGHTS OF PRESCRIBING INFORMATION

These highlights do not include all the information needed to use VENLAFAXINE HYDROCHLORIDE EXTENDED-RELEASE safely and effectively. See full prescribing information for VENLAFAXINE HYDROCHLORIDE EXTENDED-RELEASE.
Venlafaxine hydrochloride Extended-Release Capsules
Initial U.S. Approval: 1997

WARNING: SUICIDAL THOUGHTS AND BEHAVIORS

See full prescribing information for complete boxed warning.

- Increased risk of suicidal thinking and behavior in children, adolescents and young adults taking antidepressants (5.1)
- Monitor for worsening and emergence of suicidal thoughts and behaviors (5.1)
- Venlafaxine hydrochloride extended-release is not approved for use in pediatric patients (8.4)

1 INDICATIONS AND USAGE

Venlafaxine hydrochloride extended-release is a serotonin and norepinephrine reuptake inhibitor (SNRI) indicated for the treatment of:

- Major Depressive Disorder (MDD)
- Generalized Anxiety Disorder (GAD)
- Social Anxiety Disorder (SAD)
- Panic Disorder (PD)

2 DOSAGE AND ADMINISTRATION

Indication | Starting Dose | Target Dose | Maximum Dose
MDD (2.1) | 37.5 –75 mg/day | 75 mg/day | 225 mg/day
GAD (2.2) | 37.5 –75 mg/day | 75 mg/day | 225 mg/day
SAD (2.3) | 75 mg/day | 75 mg/day | 75 mg/day
PD (2.4) | 37.5 mg/day | 75 mg/day | 225 mg/day

- Take once daily with food (2). Capsules should be taken whole; do not divide, crush, chew, or dissolve (2).
- When discontinuing treatment, reduce the dose gradually (2.8, 5.7).
- Renal impairment: reduce the total daily dose by 25% to 50% in patients with renal impairment. Reduce the total daily dose by 50% or more in patients undergoing dialysis or with severe renal impairment (2.6).
- Hepatic impairment: reduce the daily dose by 50% in patients with mild to moderate hepatic impairment. In patients with severe hepatic impairment or hepatic cirrhosis, it may be necessary to reduce the dose by more than 50% (2.6).

3 DOSAGE FORMS AND STRENGTHS

- Venlafaxine hydrochloride extended-release capsules are available as 37.5 mg, 75 mg and 150 mg strengths (3).
- Each capsule contains venlafaxine hydrochloride equivalent to 37.5 mg, 75 mg or 150 mg of venlafaxine (3).

4 CONTRAINDICATIONS

- Hypersensitivity to venlafaxine hydrochloride, desvenlafaxine succinate, or any excipients in the venlafaxine hydrochloride extended-release formulation (4.1).
- Do not use with an MAOI or within 14 days of stopping an MAOI. Allow 7 days after stopping venlafaxine hydrochloride extended-release before starting an MAOI, because of the risk of serotonin syndrome (4.2, 5.2, 7.3).

5 WARNINGS AND PRECAUTIONS

- Clinical Worsening/Suicide Risk: Monitor for clinical worsening and suicide risk (5.1).
- Serotonin Syndrome: Risk increases with concomitant use of other serotonergic drugs. Discontinue venlafaxine hydrochloride extended-release and initiate supportive treatment if serotonin syndrome occurs (4.2, 5.2, 7.3).
- Elevations in Blood Pressure: Control hypertension before initiating treatment. Monitor blood pressure regularly during treatment (5.3).
- Abnormal Bleeding: Venlafaxine hydrochloride extended-release may increase risk of bleeding events. Caution patients about the risk of bleeding associated with the concomitant use of venlafaxine hydrochloride extended-release and NSAIDs, aspirin, or other drugs that affect coagulation (5.4).
- Angle Closure Glaucoma: Angle closure glaucoma has occurred in patients with untreated anatomically narrow angles treated with antidepressants. (5.5).
- Activation of Mania/Hypomania: Use cautiously in patients with bipolar disorder. Caution patients about the risk of activation of mania/hypomania (5.6).

6 ADVERSE REACTIONS

Most common adverse reactions (incidence ≥ 5% and at least twice the rate of placebo): nausea, somnolence, dry mouth, sweating, abnormal ejaculation, anorexia, constipation, erectile dysfunction, and libido decreased (6.1).

To report SUSPECTED ADVERSE REACTIONS, contact 1-800-438-1985 or FDA at 1-800-FDA-1088 or www.fda.gov/medwatch.

7 DRUG INTERACTIONS

- Serotonergic Drugs (e.g., MAOIs, triptans, SSRIs, other SNRIs, linezolid, lithium, tramadol, or St. John's wort): Potential for serotonin syndrome. Careful patient observation is advised (4.2, 5.2, 7.3).

8 USE IN SPECIFIC POPULATIONS

- Pregnancy: Based on animal data, may cause fetal harm (8.1).
- Nursing Mothers: Discontinue drug or nursing, taking into consideration importance of drug to mother (8.3).

FULL PRESCRIBING INFORMATION

WARNING: SUICIDAL THOUGHTS AND BEHAVIORS

Antidepressants increased the risk of suicidal thoughts and behavior in children, adolescents, and young adults in short-term studies. These studies did not show an increase in the risk of suicidal thoughts and behavior with antidepressant use in patients over age 24; there was a reduction in risk with antidepressant use in patients aged 65 and older [ see Warnings and Precautions (5.1)].

In patients of all ages who are started on antidepressant therapy monitor closely for clinical worsening and emergence of suicidal thoughts and behaviors. Advise families and caregivers of the need for close observation and communication with the prescriber [ see Warnings and Precautions (5.1) and Patient Counseling Information (17)].

1 INDICATIONS AND USAGE

1.1 Major Depressive Disorder

Venlafaxine hydrochloride extended-release capsules are indicated for the treatment of major depressive disorder (MDD). Efficacy was established in three short-term (4, 8, and 12 weeks) and two long-term, maintenance trials.

1.2 Generalized Anxiety Disorder

Venlafaxine hydrochloride extended-release is indicated for the treatment of Generalized Anxiety Disorder (GAD). Efficacy was established in two 8-week and two 26-week placebo-controlled trials.

1.3 Social Anxiety Disorder

Venlafaxine hydrochloride extended-release is indicated for the treatment of Social Anxiety Disorder (SAD), also known as social phobia. Efficacy was established in four 12-week and one 26-week, placebo-controlled trials.

1.4 Panic Disorder

Venlafaxine hydrochloride extended-release is indicated for the treatment of Panic Disorder (PD), with or without agoraphobia. Efficacy was established in two 12-week placebo-controlled trials.

2 DOSAGE AND ADMINISTRATION

Venlafaxine hydrochloride extended-release should be administered in a single dose with food, either in the morning or in the evening at approximately the same time each day [ see Clinical Pharmacology (12.3)]. Each capsule should be swallowed whole with fluid and not divided, crushed, chewed, or placed in water or it may be administered by carefully opening the capsule and sprinkling the entire contents on a spoonful of applesauce. This drug/food mixture should be swallowed immediately without chewing and followed with a glass of water to ensure complete swallowing of the pellets (spheroids).

2.1 Major Depressive Disorder

For most patients, the recommended starting dose for venlafaxine hydrochloride extended-release is 75 mg per day, administered in a single dose. For some patients, it may be desirable to start at 37.5 mg per day for 4 to 7 days to allow new patients to adjust to the medication before increasing to 75 mg per day. Patients not responding to the initial 75 mg per day dose may benefit from dose increases to a maximum of 225 mg per day. Dose increases should be in increments of up to 75 mg per day, as needed, and should be made at intervals of not less than 4 days, since steady-state plasma levels of venlafaxine and its major metabolites are achieved in most patients by day 4 [ see Clinical Pharmacology (12.3)]. In the clinical studies establishing efficacy, upward titration was permitted at intervals of 2 weeks or more.

It should be noted that, while the maximum recommended dose for moderately depressed outpatients is also 225 mg per day for venlafaxine hydrochloride immediate-release, more severely depressed inpatients in one study of the development program for that product responded to a mean dose of 350 mg per day (range of 150 to 375 mg per day). Whether or not higher doses of venlafaxine hydrochloride extended-release are needed for more severely depressed patients is unknown; however, the experience with venlafaxine hydrochloride extended-release doses higher than 225 mg per day is very limited.

2.2 Generalized Anxiety Disorder

For most patients, the recommended starting dose for venlafaxine hydrochloride extended-release is 75 mg per day, administered in a single dose. For some patients, it may be desirable to start at 37.5 mg per day for 4 to 7 days to allow new patients to adjust to the medication before increasing to 75 mg per day. Patients not responding to the initial 75 mg per day dose may benefit from dose increases to a maximum of 225 mg per day. Dose increases should be in increments of up to 75 mg per day, as needed, and should be made at intervals of not less than 4 days, since steady-state plasma levels of venlafaxine and its major metabolites are achieved in most patients by day 4 [ see Clinical Pharmacology (12.3)].

2.3 Social Anxiety Disorder (Social Phobia)

The recommended dose is 75 mg per day, administered in a single dose. There was no evidence that higher doses confer any additional benefit.

2.4 Panic Disorder

The recommended starting dose is 37.5 mg per day of venlafaxine hydrochloride extended-release for 7 days. Patients not responding to 75 mg per day may benefit from dose increases to a maximum of approximately 225 mg per day. Dose increases should be in increments of up to 75 mg per day, as needed, and should be made at intervals of not less than 7 days.

2.5 Switching Patients from Venlafaxine hydrochloride Immediate-Release Tablets

Depressed patients who are currently being treated at a therapeutic dose with venlafaxine hydrochloride immediate-release may be switched to venlafaxine hydrochloride extended-release at the nearest equivalent dose (mg per day), e.g., 37.5 mg venlafaxine hydrochloride immediate-release twice a day to 75 mg venlafaxine hydrochloride extended-release once daily. However, individual dosage adjustments may be necessary.

2.6 Specific Populations

Patients with Hepatic Impairment

The total daily dose should be reduced by 50% in patients with mild (Child-Pugh=5–6) to moderate (Child-Pugh=7–9) hepatic impairment. In patients with severe hepatic impairment (Child-Pugh=10–15) or hepatic cirrhosis, it may be necessary to reduce the dose by 50% or more [ See Use in Specific Populations (8.7)].

Patients with Renal Impairment

The total daily dose should be reduced by 25% to 50% in patients with mild (CLcr= 60–89 mL/min) or moderate (CLcr= 30–59 mL/min) renal impairment. In patients undergoing hemodialysis or with severe renal impairment (CLcr < 30 mL/min), the total daily dose should be reduced by 50% or more. Because there was much individual variability in clearance between patients with renal impairment, individualization of dosage may be desirable in some patients [ see Use in Specific Populations (8.7)].

2.7 Maintenance Treatment

There is no body of evidence available from controlled studies to indicate how long patients with MDD, GAD, SAD, or PD should be treated with venlafaxine hydrochloride extended-release.

It is generally agreed that acute episodes of MDD require several months or longer of sustained pharmacological therapy beyond response to the acute episode. Venlafaxine hydrochloride extended-release and venlafaxine hydrochloride immediate-release have demonstrated continuation of response in clinical studies up to 52 weeks, at the same dose at which patients responded during the initial treatment [ see Clinical Studies (14.1)]. It is not known whether or not the dose of venlafaxine hydrochloride extended-release needed for maintenance treatment is identical to the dose needed to achieve an initial response. Patients should be periodically reassessed to determine the need for maintenance treatment and the appropriate dose for such treatment.

In patients with GAD and SAD, venlafaxine hydrochloride extended-release has been shown to be effective in 6-month clinical studies. The need for continuing medication in patients with GAD and SAD who improve with venlafaxine hydrochloride extended-release treatment should be periodically reassessed.

In a clinical study for PD, patients continuing venlafaxine hydrochloride extended-release at the same dose at which they responded during the initial 12 weeks of treatment experienced a statistically significantly longer time to relapse than patients randomized to placebo [ see Clinical Studies (14.4)]. The need for continuing medication in patients with PD who improve with venlafaxine hydrochloride extended-release treatment should be periodically reassessed.

2.8 Discontinuing Venlafaxine hydrochloride Extended-Release

A gradual reduction in the dose, rather than abrupt cessation, is recommended whenever possible. In clinical studies with venlafaxine hydrochloride extended-release, tapering was achieved by reducing the daily dose by 75 mg at one-week intervals. Individualization of tapering may be necessary [ see Warnings and Precautions (5.7)].

2.9 Switching Patients to or from a Monoamine Oxidase Inhibitor (MAOI) Intended to Treat Psychiatric Disorders

At least 14 days should elapse between discontinuation of an MAOI (intended to treat psychiatric disorders) and initiation of therapy with venlafaxine hydrochloride extended-release. In addition, at least 7 days should be allowed after stopping venlafaxine hydrochloride extended-release before starting an MAOI intended to treat psychiatric disorders [ see Contraindications (4.2), Warnings and Precautions (5.2), and Drug Interactions (7.2)].

Use of Venlafaxine hydrochloride Extended-Release with other MAOIs such as Linezolid or Intravenous Methylene Blue

Do not start venlafaxine hydrochloride extended-release in a patient who is being treated with linezolid or intravenous methylene blue, because there is an increased risk of serotonin syndrome. In a patient who requires more urgent treatment of a psychiatric condition, other interventions, including hospitalization should be considered [ see Contraindications (4.2)].

In some cases, a patient already receiving venlafaxine hydrochloride extended-release therapy may require urgent treatment with linezolid or intravenous methylene blue. If acceptable alternatives to linezolid or intravenous methylene blue are not available and the potential benefits of linezolid or intravenous methylene blue treatment are judged to outweigh the risks of serotonin syndrome in a particular patient, venlafaxine hydrochloride extended-release should be stopped promptly, and linezolid or intravenous methylene blue can be administered. Monitor the patient for symptoms of serotonin syndrome for 7 days or until 24 hours after the last dose of linezolid or intravenous methylene blue, whichever comes first. Therapy with venlafaxine hydrochloride extended-release can be resumed 24 hours after the last dose of linezolid or intravenous methylene blue [ see Warnings and Precautions (5.2)].

The risk of administering methylene blue by non-intravenous routes (such as oral tablets or by local injection) or in intravenous doses much lower than 1 mg/kg concomitantly with venlafaxine hydrochloride extended-release is unclear. The clinician should, nevertheless, be aware of the possibility of emergent symptoms of serotonin syndrome with such use [ see Warnings and Precautions (5.2)] .

3 DOSAGE FORMS AND STRENGTHS

Venlafaxine hydrochloride extended-release capsules are available in the following strengths:

- 37.5 mg capsules (grey cap/peach body with " W " and "Effexor XR" on the cap and "37.5" on the body)
- 75 mg capsules (peach cap and body with " W " and "Effexor XR" on the cap and "75" on the body)
- 150 mg capsules (dark orange cap and body with " W " and "Effexor XR" on the cap and "150" on the body)

4 CONTRAINDICATIONS

4.1 Hypersensitivity

Hypersensitivity to venlafaxine hydrochloride, desvenlafaxine succinate or to any excipients in the formulation

4.2 Concomitant Use with Monoamine Oxidase Inhibitors (MAOIs)

The use of MAOIs (intended to treat psychiatric disorders) concomitantly with venlafaxine hydrochloride extended-release or within 7 days of discontinuing treatment with venlafaxine hydrochloride extended-release is contraindicated because of an increased risk of serotonin syndrome. The use of venlafaxine hydrochloride extended-release within 14 days of discontinuing treatment with an MAOI (intended to treat psychiatric disorders) is also contraindicated [ see Dosage and Administration (2.9), Warnings and Precautions (5.2), and Drug Interactions (7.2)] .

Starting venlafaxine hydrochloride extended-release in a patient who is being treated with an MAOI such as linezolid or intravenous methylene blue is also contraindicated, because of an increased risk of serotonin syndrome [ see Dosage and Administration (2.9), Warnings and Precautions (5.2), and Drug Interactions (7.3)].

5 WARNINGS AND PRECAUTIONS

5.1 Suicidal Thoughts and Behaviors in Children, Adolescents, and Young Adults

Patients with major depressive disorder (MDD), both adult and pediatric, may experience worsening of their depression and/or the emergence of suicidal ideation and behavior (suicidality) or unusual changes in behavior, whether or not they are taking antidepressant medications, and this risk may persist until significant remission occurs. Suicide is a known risk of depression and certain other psychiatric disorders, and these disorders themselves are the strongest predictors of suicide. There has been a long-standing concern, however, that antidepressants may have a role in inducing worsening of depression and the emergence of suicidality in certain patients during the early phases of treatment. Pooled analyses of short-term placebo-controlled studies of antidepressant drugs (SSRIs and others) showed that these drugs increase the risk of suicidal thinking and behavior (suicidality) in children, adolescents, and young adults (ages 18–24) with MDD and other psychiatric disorders. Short-term studies did not show an increase in the risk of suicidality with antidepressants compared to placebo in adults beyond age 24; there was a reduction with antidepressants compared to placebo in adults aged 65 and older.

The pooled analyses of placebo-controlled studies in children and adolescents with MDD, Obsessive Compulsive Disorder (OCD), or other psychiatric disorders included a total of 24 short-term studies of 9 antidepressant drugs in over 4,400 patients. The pooled analyses of placebo-controlled studies in adults with MDD or other psychiatric disorders included a total of 295 short-term studies (median duration of 2 months) of 11 antidepressant drugs in over 77,000 patients. There was considerable variation in risk of suicidality among drugs, but a tendency toward an increase in the younger patients for almost all drugs studied. There were differences in absolute risk of suicidality across the different indications, with the highest incidence in MDD. The risk differences (drug versus placebo), however, were relatively stable within age strata and across indications. These risk differences (drug-placebo difference in the number of cases of suicidality per 1,000 patients treated) are provided in Table 1.

Table 1: Difference in the Number of Cases of Suicidality per 1,000 Patients Treated versus Placebo
Age Range | Increases Compared to Placebo
< 18 | 14 additional cases
18–24 | 5 additional cases
 | Decreases Compared to Placebo
25–64 | 1 fewer case
≥ 65 | 6 fewer cases

No suicides occurred in any of the pediatric studies. There were suicides in the adult studies, but the number was not sufficient to reach any conclusion about drug effect on suicide.

It is unknown whether the suicidality risk extends to longer term use, i.e., beyond several months. However, there is substantial evidence from placebo-controlled maintenance studies in adults with depression that the use of antidepressants can delay the recurrence of depression.

All patients being treated with antidepressants for any indication should be monitored appropriately and observed closely for clinical worsening, suicidality, and unusual changes in behavior, especially during the initial few months of a course of drug therapy, or at times of dose changes, either increases or decreases.

The following symptoms, anxiety, agitation, panic attacks, insomnia, irritability, hostility, aggressiveness, impulsivity, akathisia (psychomotor restlessness), hypomania, and mania, have been reported in adult and pediatric patients being treated with antidepressants for MDD, as well as for other indications, both psychiatric and nonpsychiatric. Although a causal link between the emergence of such symptoms and either the worsening of depression and/or the emergence of suicidal impulses has not been established, there is concern that such symptoms may represent precursors to emerging suicidality.

Consideration should be given to changing the therapeutic regimen, including possibly discontinuing the medication, in patients whose depression is persistently worse, or who are experiencing emergent suicidality or symptoms that might be precursors to worsening depression or suicidality, especially if these symptoms are severe, abrupt in onset, or were not part of the patient's presenting symptoms.

If the decision has been made to discontinue treatment, medication should be tapered, as rapidly as is feasible, but with recognition that abrupt discontinuation can be associated with certain symptoms [ see Warnings and Precautions (5.7) and Dosage and Administration (2.8)].

Families and caregivers of patients being treated with antidepressants for MDD or other indications, both psychiatric and nonpsychiatric, should be alerted about the need to monitor patients for the emergence of agitation, irritability, unusual changes in behavior, and the other symptoms described above, as well as the emergence of suicidality, and to report such symptoms immediately to healthcare providers. Such monitoring should include daily observation by families and caregivers . Prescriptions for venlafaxine hydrochloride extended-release should be written for the smallest quantity of capsules consistent with good patient management, in order to reduce the risk of overdose.

Screening Patients for Bipolar Disorder

A major depressive episode may be the initial presentation of bipolar disorder. It is generally believed (though not established in controlled studies) that treating such an episode with an antidepressant alone may increase the likelihood of precipitation of a mixed/manic episode in patients at risk for bipolar disorder. Whether any of the symptoms described above represent such a conversion is unknown. However, prior to initiating treatment with an antidepressant, patients with depressive symptoms should be adequately screened to determine if they are at risk for bipolar disorder; such screening should include a detailed psychiatric history, including a family history of suicide, bipolar disorder, and depression. It should be noted that venlafaxine hydrochloride extended-release is not approved for use in treating bipolar depression.

5.2 Serotonin Syndrome

The development of a potentially life-threatening serotonin syndrome has been reported with SNRIs and SSRIs, including venlafaxine hydrochloride extended-release alone, but particularly with concomitant use of other serotonergic drugs (including triptans, tricyclic antidepressants, fentanyl, lithium, tramadol, tryptophan, buspirone, and St. John's wort) and with drugs that impair metabolism of serotonin in particular, MAOIs, both those intended to treat psychiatric disorders and others, such as linezolid or intravenous methylene blue).

Serotonin syndrome symptoms may include mental status changes (e.g., agitation, hallucinations, delirium, coma) autonomic instability (e.g., tachycardia, labile blood pressure, hyperthermia, diaphoresis, flushing, and dizziness), neuromuscular symptoms (e.g., tremor, rigidity, myoclonus, hyperreflexia, incoordination); seizures and gastrointestinal symptoms (e.g., nausea, vomiting, diarrhea). Patients should be monitored for the emergence of serotonin syndrome.

The concomitant use of venlafaxine hydrochloride extended-release with MAOIs (intended to treat psychiatric disorders) is contraindicated. Venlafaxine hydrochloride extended-release should also not be started in a patient who is being treated with MAOIs such as linezolid or intravenous methylene blue. All reports with methylene blue that provided information on the route of administration involved intravenous administration in the dose range of 1 mg/kg to 8 mg/kg. No reports involved the administration of methylene blue by other routes (such as oral tablets or local tissue injection) or at lower doses. There may be circumstances when it is necessary to initiate treatment with a MAOI such as linezolid or intravenous methylene blue in a patient taking venlafaxine hydrochloride extended-release. Venlafaxine hydrochloride extended-release should be discontinued before initiating treatment with the MAOI [ see Contraindications (4.2), Dosage and Administration (2.6), and Drug Interactions (7.3)].

If concomitant use of venlafaxine hydrochloride extended-release with other serotonergic drugs (e.g., triptans, tricyclic antidepressants, mirtazapine, fentanyl, lithium, tramadol, buspirone, tryptophan, or St. John's wort) is clinically warranted, careful observation of the patient is advised, particularly during treatment initiation and dose increases [ see Drug Interactions (7.3)]. Patients should be made aware of the potential risk of serotonin syndrome. Treatment with venlafaxine hydrochloride extended-release and any concomitant serotonergic agents should be discontinued immediately if the above events occur, and supportive symptomatic treatment should be initiated.

5.3 Elevations in Blood Pressure

In controlled trials, there were dose-related increases in systolic and diastolic blood pressure, as well as cases of sustained hypertension [ see Adverse Reactions (6.2)] .

Monitor blood pressure before initiating treatment with venlafaxine hydrochloride extended-release and regularly during treatment. Control pre-existing hypertension before initiating treatment with venlafaxine hydrochloride extended-release. Use caution in treating patients with pre-existing hypertension or cardiovascular or cerebrovascular conditions that might be compromised by increases in blood pressure. Sustained blood pressure elevation can lead to adverse outcomes. Cases of elevated blood pressure requiring immediate treatment have been reported with venlafaxine hydrochloride extended-release. Consider dose reduction or discontinuation of treatment for patients who experience a sustained increase in blood pressure.

Across all clinical studies with venlafaxine, 1.4% of patients in the venlafaxine hydrochloride extended-release treated groups experienced a ≥15 mm Hg increase in supine diastolic blood pressure (SDBP) ≥ 105 mm Hg, compared to 0.9% of patients in the placebo groups. Similarly, 1% of patients in the venlafaxine hydrochloride extended-release treated groups experienced a ≥ 20 mm Hg increase in supine systolic blood pressure (SSBP) with blood pressure ≥ 180 mm Hg, compared to 0.3% of patients in the placebo groups [ see Table 10 in Adverse Reactions (6.2)]. Venlafaxine hydrochloride extended-release treatment was associated with sustained hypertension (defined as treatment-emergent SDBP ≥ 90 mm Hg and ≥ 10 mm Hg above baseline for three consecutive on-therapy visits [ see Table 11 in Adverse Reactions (6.2)]. An insufficient number of patients received mean doses of venlafaxine hydrochloride extended-release over 300 mg per day in clinical studies to fully evaluate the incidence of sustained increases in blood pressure at these higher doses.

5.4 Abnormal Bleeding

SSRIs and SNRIs, including venlafaxine hydrochloride extended-release, may increase the risk of bleeding events, ranging from ecchymoses, hematomas, epistaxis, petechiae, and gastrointestinal hemorrhage to life-threatening hemorrhage. Concomitant use of aspirin, Nonsteroidal Anti-Inflammatory Drugs (NSAIDs), warfarin, and other anti-coagulants or other drugs known to affect platelet function may add to this risk. Case reports and epidemiological studies (case-control and cohort design) have demonstrated an association between use of drugs that interfere with serotonin reuptake and the occurrence of gastrointestinal bleeding. Caution patients about the risk of bleeding associated with the concomitant use of venlafaxine hydrochloride extended-release and NSAIDs, aspirin, or other drugs that affect coagulation.

5.5 Angle-Closure Glaucoma

The pupillary dilation that occurs following use of many antidepressant drugs including venlafaxine hydrochloride extended-release may trigger an angle closure attack in a patient with anatomically narrow angles who does not have a patent iridectomy.

5.6 Activation of Mania/Hypomania

Mania or hypomania was reported in venlafaxine hydrochloride extended-release treated patients in the premarketing studies in MDD, SAD, and PD (see Table 2). Mania/hypomania has also been reported in a small proportion of patients with mood disorders who were treated with other marketed drugs to treat MDD. Venlafaxine hydrochloride extended-release should be used cautiously in patients with a history of mania or hypomania.

Table 2: Incidence (%) of Mania or Hypomania Reported in Venlafaxine hydrochloride Extended-Release Treated Patients in the Premarketing Studies
Indication | Venlafaxine hydrochloride Extended-Release | Placebo
MDD | 0.3 | 0.0
GAD | 0.0 | 0.2
SAD | 0.2 | 0.0
PD | 0.1 | 0.0

5.7 Discontinuation Syndrome

Discontinuation symptoms have been systematically evaluated in patients taking venlafaxine, including prospective analyses of clinical studies in GAD and retrospective surveys of studies in MDD and SAD. Abrupt discontinuation or dose reduction of venlafaxine at various doses has been found to be associated with the appearance of new symptoms, the frequency of which increased with increased dose level and with longer duration of treatment. Reported symptoms include agitation, anorexia, anxiety, confusion, impaired coordination and balance, diarrhea, dizziness, dry mouth, dysphoric mood, fasciculation, fatigue, flu-like symptoms, headaches, hypomania, insomnia, nausea, nervousness, nightmares, sensory disturbances (including shock-like electrical sensations), somnolence, sweating, tremor, vertigo, and vomiting.

During marketing of venlafaxine hydrochloride extended-release, other SNRIs, and SSRIs, there have been spontaneous reports of adverse events occurring upon discontinuation of these drugs, particularly when abrupt, including the following: dysphoric mood, irritability, agitation, dizziness, sensory disturbances (e.g., paresthesia, such as electric shock sensations), anxiety, confusion, headache, lethargy, emotional lability, insomnia, hypomania, tinnitus, and seizures. While these events are generally self-limiting, there have been reports of serious discontinuation symptoms.

Patients should be monitored for these symptoms when discontinuing treatment with venlafaxine hydrochloride extended-release. A gradual reduction in the dose, rather than abrupt cessation, is recommended whenever possible. If intolerable symptoms occur following a decrease in the dose or upon discontinuation of treatment, then resuming the previously prescribed dose may be considered. Subsequently, the physician may continue decreasing the dose, but at a more gradual rate [ see Dosage and Administration (2.8)].

5.8 Seizures

Seizures have occurred with venlafaxine therapy. Venlafaxine hydrochloride extended-release, like many antidepressants, should be used cautiously in patients with a history of seizures and should be discontinued in any patient who develops seizures. [Must mitigate the risk: Risk factors, concomitant meds that lower the seizure threshold.]

5.9 Hyponatremia

Hyponatremia can occur as a result of treatment with SSRIs and SNRIs, including venlafaxine hydrochloride extended-release. In many cases, the hyponatremia appears to be the result of the Syndrome of Inappropriate Antidiuretic Hormone (SIADH) secretion. Cases with serum sodium lower than 110 mmol/L have been reported. Elderly patients may be at greater risk of developing hyponatremia with SSRIs and SNRIs [ see Use in Specific Populations (8.5)]. Also, patients taking diuretics, or those who are otherwise volume-depleted, may be at greater risk. Consider discontinuation of venlafaxine hydrochloride extended-release in patients with symptomatic hyponatremia, and institute appropriate medical intervention.

Signs and symptoms of hyponatremia include headache, difficulty concentrating, memory impairment, confusion, weakness, and unsteadiness, which may lead to falls. Signs and symptoms associated with more severe and/or acute cases have included hallucination, syncope, seizure, coma, respiratory arrest, and death.

5.10 Weight and Height Changes in Pediatric Patients

Weight Changes

The average change in body weight and incidence of weight loss (percentage of patients who lost 3.5% or more) in the placebo-controlled pediatric studies in MDD, GAD, and SAD are shown in Tables 3 and 4.

Table 3: Average Change in Body Weight (kg) From Beginning of Treatment in Pediatric Patients in Double-blind, Placebo-controlled Studies of Venlafaxine hydrochloride Extended-Release
Indication (Duration) | Venlafaxine hydrochloride Extended-Release | Placebo
MDD and GAD (4 pooled studies, 8 weeks) | -0.45 (n = 333) | +0.77 (n = 333)
SAD (16 weeks) | -0.75 (n = 137) | +0.76 (n = 148)

Table 4: Incidence (%) of Pediatric Patients Experiencing Weight Loss (3.5% or more) in Double-blind, Placebo-controlled Studies of Venlafaxine hydrochloride Extended-Release
Indication (Duration) | Venlafaxine hydrochloride Extended-Release | Placebo
MDD and GAD (4 pooled studies, 8 weeks) | 18 [p < 0.001 versus placebo] (n = 333) | 3.6 (n = 333)
SAD (16 weeks) | 47 (n = 137) | 14 (n = 148)

Weight loss was not limited to patients with treatment-emergent anorexia [ see Warnings and Precautions (5.11)].

The risks associated with longer term venlafaxine hydrochloride extended-release use were assessed in an open-label MDD study of children and adolescents who received venlafaxine hydrochloride extended-release for up to six months. The children and adolescents in the study had increases in weight that were less than expected, based on data from age- and sex-matched peers. The difference between observed weight gain and expected weight gain was larger for children (< 12 years old) than for adolescents (≥ 12 years old).

Height Changes

Table 5 shows the average height increase in pediatric patients in the short-term, placebo-controlled MDD, GAD, and SAD studies. The differences in height increases in GAD and MDD studies were most notable in patients younger than twelve.

Table 5: Average Height Increases (cm) in Pediatric Patients in Placebo-controlled Studies of Venlafaxine hydrochloride Extended-Release
Indication (Duration) | Venlafaxine hydrochloride Extended-Release | Placebo
MDD
(8 weeks) | 0.8 (n = 146) | 0.7 (n = 147)
GAD
(8 weeks) | 0.3 [p = 0.041] (n = 122) | 1.0 (n = 132)
SAD
(16 weeks) | 1.0 (n = 109) | 1.0 (n = 112)

In the six-month, open-label MDD study, children and adolescents had height increases that were less than expected, based on data from age- and sex-matched peers. The difference between observed and expected growth rates was larger for children (< 12 years old) than for adolescents (≥ 12 years old).

5.11 Appetite Changes in Pediatric Patients

Decreased appetite (reported as treatment-emergent anorexia) was more commonly observed in venlafaxine hydrochloride extended-release treated patients versus placebo-treated patients in the premarketing evaluation of venlafaxine hydrochloride extended-release for MDD, GAD, and SAD (see Table 6).

Table 6: Incidence (%) of Decreased Appetite and Associated Discontinuation Rates [The discontinuation rates for weight loss were 0.7% for patients receiving either venlafaxine hydrochloride extended-release or placebo.] (%) in Pediatric Patients in Placebo-controlled Studies of Venlafaxine hydrochloride Extended-Release
Indication | Venlafaxine hydrochloride Extended-Release |  | Placebo
(Duration) | Incidence | Discontinuation | Incidence | Discontinuation
MDD and GAD (pooled, 8 weeks) | 10 | 0.0 | 3 | –
SAD (16 weeks) | 22 | 0.7 | 3 | 0.0

5.12 Interstitial Lung Disease and Eosinophilic Pneumonia

Interstitial lung disease and eosinophilic pneumonia associated with venlafaxine therapy have been rarely reported. The possibility of these adverse events should be considered in venlafaxine-treated patients who present with progressive dyspnea, cough or chest discomfort. Such patients should undergo a prompt medical evaluation, and discontinuation of venlafaxine therapy should be considered.

6 ADVERSE REACTIONS

The following adverse reactions are discussed in greater detail in other sections of the label:

- Hypersensitivity [ see Contraindications (4.1)]
- Suicidal Thoughts and Behaviors in Children, Adolescents, and Adults [ see Warnings and Precautions (5.1)]
- Serotonin Syndrome [ see Warnings and Precautions (5.2)]
- Elevations in Blood Pressure [ see Warnings and Precautions (5.3)]
- Abnormal Bleeding [ see Warnings and Precautions (5.4)]
- Angle Closure Glaucoma [ see Warnings and Precautions (5.5)]
- Activation of Mania/Hypomania [ see Warnings and Precautions (5.6)]
- Discontinuation Syndrome [ see Warnings and Precautions (5.7)]
- Renal Impairment [ see Warnings and Precautions (2.6)]
- Hepatic Impairment [ see Warnings and Precautions (2.6)]
- Seizure [ see Warnings and Precautions (5.8)]
- Hyponatremia [ see Warnings and Precautions (5.9)]
- Weight and Height changes in Pediatric Patients [ see Warnings and Precautions (5.10)]
- Appetite Changes in Pediatric Patients [ see Warnings and Precautions (5.11)]
- Interstitial Lung Disease and Eosinophilic Pneumonia [ see Warnings and Precautions (5.12)]

6.1 Clinical Studies Experience

Because clinical studies are conducted under widely varying conditions, adverse reaction rates observed in the clinical studies of a drug cannot be directly compared to rates in the clinical studies of another drug and may not reflect the rates observed in practice.

Most Common Adverse Reactions

The most commonly observed adverse reactions in the clinical study database in venlafaxine hydrochloride extended-release treated patients in MDD, GAD, SAD, and PD (incidence ≥ 5% and at least twice the rate of placebo) were: nausea (30.0%), somnolence (15.3%), dry mouth (14.8%), sweating (11.4%), abnormal ejaculation (9.9%), anorexia (9.8%), constipation (9.3%), impotence (5.3%) and decreased libido (5.1%).

Adverse Reactions Reported as Reasons for Discontinuation of Treatment

Combined across short-term, placebo-controlled premarketing studies for all indications, 12% of the 3,558 patients who received venlafaxine hydrochloride extended-release (37.5–225 mg) discontinued treatment due to an adverse experience, compared with 4% of the 2,197 placebo-treated patients in those studies.

The most common adverse reactions leading to discontinuation in ≥ 1% of the venlafaxine hydrochloride extended-release treated patients in the short-term studies (up to 12 weeks) across indications are shown in Table 7.

Table 7: Incidence (%) of Patients Reporting Adverse Reactions Leading to Discontinuation in Placebo-controlled Clinical Studies (up to 12 Weeks Duration)
Body System Adverse Reaction | Venlafaxine hydrochloride Extended-Release n = 3,558 | Placebo n = 2,197
Body as a whole
Asthenia | 1.7 | 0.5
Headache | 1.5 | 0.8
Digestive system
Nausea | 4.3 | 0.4
Nervous system
Dizziness | 2.2 | 0.8
Insomnia | 2.1 | 0.6
Somnolence | 1.7 | 0.3
Skin and appendages | 1.5 | 0.6
Sweating | 1.0 | 0.2

Common Adverse Reactions in Placebo-controlled Studies

The number of patients receiving multiple doses of venlafaxine hydrochloride extended-release during the premarketing assessment for each approved indication is shown in Table 8. The conditions and duration of exposure to venlafaxine in all development programs varied greatly, and included (in overlapping categories) open and double-blind studies, uncontrolled and controlled studies, inpatient (venlafaxine hydrochloride immediate-release only) and outpatient studies, fixed-dose, and titration studies.

Table 8: Patients Receiving Venlafaxine hydrochloride Extended-Release in Premarketing Clinical Studies
Indication | Venlafaxine hydrochloride Extended-Release
MDD | 705 [In addition, in the premarketing assessment of venlafaxine hydrochloride immediate-release, multiple doses were administered to 2,897 patients in studies for MDD.]
GAD | 1,381
SAD | 819
PD | 1,314

The incidences of common adverse reactions (those that occurred in ≥ 2% of venlafaxine hydrochloride extended-release treated patients [357 MDD patients, 1,381 GAD patients, 819 SAD patients, and 1,001 PD patients] and more frequently than placebo) in venlafaxine hydrochloride extended-release treated patients in short-term, placebo-controlled, fixed- and flexible-dose clinical studies (doses 37.5 to 225 mg per day) are shown in Table 9.

The adverse reaction profile did not differ substantially between the different patient populations.

Table 9: Common Adverse Reactions: Percentage of Patients Reporting Adverse Reactions (≥ 2% and > placebo) in Placebo-controlled Studies (up to 12 Weeks Duration) across All Indications
Body System Adverse Reaction | Venlafaxine hydrochloride Extended-Release n = 3,558 | Placebo n = 2,197
Body as a whole
Asthenia | 12.6 | 7.8
Cardiovascular system
Hypertension | 3.4 | 2.6
Palpitation | 2.2 | 2.0
Vasodilatation | 3.7 | 1.9
Digestive system
Anorexia | 9.8 | 2.6
Constipation | 9.3 | 3.4
Diarrhea | 7.7 | 7.2
Dry mouth | 14.8 | 5.3
Nausea | 30.0 | 11.8
Vomiting | 4.3 | 2.7
Nervous system
Abnormal dreams | 2.9 | 1.4
Dizziness | 15.8 | 9.5
Insomnia | 17.8 | 9.5
Libido decreased | 5.1 | 1.6
Nervousness | 7.1 | 5.0
Paresthesia | 2.4 | 1.4
Somnolence | 15.3 | 7.5
Tremor | 4.7 | 1.6
Respiratory system
Yawn | 3.7 | 0.2
Skin and appendages
Sweating (including night sweats) | 11.4 | 2.9
Special senses
Abnormal vision | 4.2 | 1.6
Urogenital system
Abnormal ejaculation/orgasm (men) [Percentages based on the number of men (venlafaxine hydrochloride extended-release, n = 1,440; placebo, n = 923)] | 9.9 | 0.5
Anorgasmia (men) | 3.6 | 0.1
Anorgasmia (women) [Percentages based on the number of women (venlafaxine hydrochloride extended-release, n = 2,118; placebo, n = 1,274)] | 2.0 | 0.2
Impotence (men) | 5.3 | 1.0

Other Adverse Reactions Observed in Clinical Studies

Body as a whole – Photosensitivity reaction, chills

Cardiovascular system – Postural hypotension, syncope, hypotension, tachycardia

Digestive system – Gastrointestinal hemorrhage [ see Warnings and Precautions (5.4)], bruxism

Hemic/Lymphatic system – Ecchymosis [ see Warnings and Precautions (5.4)]

Metabolic/Nutritional – Hypercholesterolemia, weight gain [ see Warnings and Precautions (5.10)], weight loss [ see Warnings and Precautions (5.10)]

Nervous system – Seizures [ see Warnings and Precautions (5.8)], manic reaction [ see Warnings and Precautions (5.6)], agitation, confusion, akathisia, hallucinations, hypertonia, myoclonus, depersonalization, apathy

Skin and appendages – Urticaria, pruritus, rash, alopecia

Special senses – Mydriasis, abnormality of accommodation, tinnitus, taste perversion

Urogenital system – Urinary retention, urination impaired, urinary incontinence, urinary frequency increased, menstrual disorders associated with increased bleeding or increased irregular bleeding (e.g., menorrhagia, metrorrhagia)

6.2 Vital Sign Changes

In placebo-controlled premarketing studies, there were increases in mean blood pressure (see Table 10). Across most indications, a dose-related increase in mean supine systolic and diastolic blood pressure was evident in patients treated with venlafaxine hydrochloride extended-release. Across all clinical studies in MDD, GAD, SAD and PD, 1.4% of patients in the venlafaxine hydrochloride extended-release groups experienced an increase in SDBP of ≥15 mm Hg along with a blood pressure ≥ 105 mm Hg, compared to 0.9% of patients in the placebo groups. Similarly, 1% of patients in the venlafaxine hydrochloride extended-release groups experienced an increase in SSBP of ≥ 20 mm Hg with a blood pressure ≥ 180 mm Hg, compared to 0.3% of patients in the placebo groups.

Table 10: Final On-therapy Mean Changes From Baseline in Supine Systolic (SSBP) and Diastolic (SDBP) Blood Pressure (mm Hg) in Placebo-controlled Studies
 | Venlafaxine hydrochloride Extended-Release |  |  |  | Placebo
Indication | ≤ 75 mg per day |  | > 75 mg per day
(Duration) | SSBP | SDBP | SSBP | SDBP | SSBP | SDBP
MDD
(8–12 weeks) | -0.28 | 0.37 | 2.93 | 3.56 | -1.08 | -0.10
GAD
(8 weeks) | -0.28 | 0.02 | 2.40 | 1.68 | -1.26 | -0.92
(6 months) | 1.27 | -0.69 | 2.06 | 1.28 | -1.29 | -0.74
SAD
(12 weeks) | -0.29 | -1.26 | 1.18 | 1.34 | -1.96 | -1.22
(6 months) | -0.98 | -0.49 | 2.51 | 1.96 | -1.84 | -0.65
PD
(10–12 weeks) | -1.15 | 0.97 | -0.36 | 0.16 | -1.29 | -0.99

Venlafaxine hydrochloride extended-release treatment was associated with sustained hypertension (defined as treatment-emergent Supine Diastolic Blood Pressure [SDBP] ≥ 90 mm Hg and ≥ 10 mm Hg above baseline for three consecutive on-therapy visits (see Table 11). An insufficient number of patients received mean doses of venlafaxine hydrochloride extended-release over 300 mg per day in clinical studies to fully evaluate the incidence of sustained increases in blood pressure at these higher doses.

Table 11: Sustained Elevations in SDBP in Venlafaxine hydrochloride Extended-Release Premarketing Studies
Indication | Dose Range (mg per day) | Incidence (%)
MDD | 75–375 | 19/705 (3)
GAD | 37.5–225 | 5/1011 (0.5)
SAD | 75–225 | 5/771 (0.6)
PD | 75–225 | 9/973 (0.9)

Venlafaxine hydrochloride extended-release was associated with mean increases in pulse rate compared with placebo in premarketing placebo-controlled studies (see Table 12) [ see Warnings and Precautions (5.3, 5.4)].

Table 12: Approximate Mean Final On-therapy Increase in Pulse Rate (beats/min) in Venlafaxine hydrochloride Extended-Release Premarketing Placebo-controlled Studies (up to 12 Weeks Duration)
Indication (Duration) | Venlafaxine hydrochloride Extended-Release | Placebo
MDD
(12 weeks) | 2 | 1
GAD
(8 weeks) | 2 | < 1
SAD
(12 weeks) | 3 | 1
PD
(12 weeks) | 1 | < 1

6.3 Laboratory Changes

Serum Cholesterol

Venlafaxine hydrochloride extended-release was associated with mean final increases in serum cholesterol concentrations compared with mean final decreases for placebo in premarketing MDD, GAD, SAD and PD clinical studies (Table 13).

Table 13: Mean Final On-therapy Changes in Cholesterol Concentrations (mg/dL) in Venlafaxine hydrochloride Extended-Release Premarketing Studies
Indication (Duration) | Venlafaxine hydrochloride Extended-Release | Placebo
MDD
(12 weeks) | +1.5 | -7.4
GAD
(8 weeks) | +1.0 | -4.9
(6 months) | +2.3 | -7.7
SAD
(12 weeks) | +7.9 | -2.9
(6 months) | +5.6 | -4.2
PD
(12 weeks) | 5.8 | -3.7

Venlafaxine hydrochloride extended-release capsules treatment for up to 12 weeks in premarketing placebo-controlled trials for major depressive disorder was associated with a mean final on-therapy increase in serum cholesterol concentration of approximately 1.5 mg/dL compared with a mean final decrease of 7.4 mg/dL for placebo. Venlafaxine hydrochloride extended-release treatment for up to 8 weeks and up to 6 months in premarketing placebo-controlled GAD trials was associated with mean final on-therapy increases in serum cholesterol concentration of approximately 1.0 mg/dL and 2.3 mg/dL, respectively while placebo subjects experienced mean final decreases of 4.9 mg/dL and 7.7 mg/dL, respectively. Venlafaxine hydrochloride extended-release treatment for up to 12 weeks and up to 6 months in premarketing placebo-controlled Social Anxiety Disorder trials was associated with mean final on-therapy increases in serum cholesterol concentration of approximately 7.9 mg/dL and 5.6 mg/dL, respectively, compared with mean final decreases of 2.9 and 4.2 mg/dL, respectively, for placebo. Venlafaxine hydrochloride extended-release treatment for up to 12 weeks in premarketing placebo-controlled panic disorder trials was associated with mean final on-therapy increases in serum cholesterol concentration of approximately 5.8 mg/dL compared with a mean final decrease of 3.7 mg/dL for placebo.

Patients treated with venlafaxine hydrochloride immediate-release for at least 3 months in placebo-controlled 12-month extension trials had a mean final on-therapy increase in total cholesterol of 9.1 mg/dL compared with a decrease of 7.1 mg/dL among placebo-treated patients. This increase was duration dependent over the study period and tended to be greater with higher doses. Clinically relevant increases in serum cholesterol, defined as 1) a final on-therapy increase in serum cholesterol ≥50 mg/dL from baseline and to a value ≥261 mg/dL, or 2) an average on-therapy increase in serum cholesterol ≥50 mg/dL from baseline and to a value ≥261 mg/dL, were recorded in 5.3% of venlafaxine-treated patients and 0.0% of placebo-treated patients.

Serum Triglycerides

Venlafaxine hydrochloride extended-release was associated with mean final on-therapy increases in fasting serum triglycerides compared with placebo in premarketing clinical studies of SAD and PD up to 12 weeks (pooled data) and 6 months duration (Table 14).

Table 14: Mean Final On-therapy Increases in Triglyceride Concentrations (mg/dL) in Venlafaxine hydrochloride Extended-Release Premarketing Studies
Indication (Duration) | Venlafaxine hydrochloride Extended-Release | Placebo
SAD | 8.2 | 0.4
(12 weeks)
SAD | 11.8 | 1.8
(6 months)
PD | 5.9 | 0.9
(12 weeks)
PD | 9.3 | 0.3
(6 months)

6.4 Pediatric Patients

In general, the adverse reaction profile of venlafaxine (in placebo-controlled clinical studies) in children and adolescents (ages 6 to 17) was similar to that seen for adults. As with adults, decreased appetite, weight loss, increased blood pressure, and increased serum cholesterol were observed [ see Warnings and Precautions (5.3, 5.10, 5.11) and Use in Specific Populations (8.4)].

In pediatric clinical studies, the adverse reaction, suicidal ideation, was observed.

Particularly, the following adverse reactions were observed in pediatric patients: abdominal pain, agitation, dyspepsia, ecchymosis, epistaxis, and myalgia.

6.5 Adverse Reactions Identified During Postapproval Use

The following adverse reactions have been identified during postapproval use of venlafaxine hydrochloride extended-release. Because these reactions are reported voluntarily from a population of uncertain size, it is not always possible to reliably estimate their frequency or establish a causal relationship to drug exposure:

Body as a whole – Anaphylaxis, angioedema

Cardiovascular system – QT prolongation, ventricular fibrillation, ventricular tachycardia (including torsade de pointes)

Digestive system – Pancreatitis

Hemic/Lymphatic system – Mucous membrane bleeding [ see Warnings and Precautions (5.4)], blood dyscrasias (including agranulocytosis, aplastic anemia, neutropenia and pancytopenia), prolonged bleeding time, thrombocytopenia

Metabolic/Nutritional – Hyponatremia [ see Warnings and Precautions (5.9)], Syndrome of Inappropriate Antidiuretic Hormone (SIADH) secretion [ see Warnings and Precautions (5.9)], abnormal liver function tests, hepatitis, prolactin increased

Musculoskeletal – Rhabdomyolysis

Nervous system – Neuroleptic Malignant Syndrome (NMS) [ see Warnings and Precautions (5.2)], serotonergic syndrome [ see Warnings and Precautions (5.2)], delirium, extrapyramidal reactions (including dystonia and dyskinesia), impaired coordination and balance, tardive dyskinesia

Respiratory system – Dyspnea, interstitial lung disease, pulmonary eosinophilia [ see Warnings and Precautions (5.12)]

Skin and appendages – Stevens-Johnson syndrome, toxic epidermal necrolysis, erythema multiforme

Special senses – Angle-closure glaucoma [ see Warnings and Precautions (5.5)]

7 DRUG INTERACTIONS

7.1 Central Nervous System (CNS)-Active Drugs

The risk of using venlafaxine in combination with other CNS-active drugs has not been systematically evaluated. Consequently, caution is advised when venlafaxine hydrochloride extended-release is taken in combination with other CNS-active drugs.

7.2 Monoamine Oxidase Inhibitors

Adverse reactions, some of which were serious, have been reported in patients who have recently been discontinued from an MAOI and started on antidepressants with pharmacological properties similar to venlafaxine hydrochloride extended-release (SNRIs or SSRIs), or who have recently had SNRI or SSRI therapy discontinued prior to initiation of an MAOI [ see Dosage and Administration (2.9), Contraindications (4.2) and Warnings and Precautions (5.2)].

7.3 Serotonergic Drugs

Based on the mechanism of action of venlafaxine hydrochloride extended-release and the potential for serotonin syndrome, caution is advised when venlafaxine hydrochloride extended-release is coadministered with other drugs that may affect the serotonergic neurotransmitter systems, such as triptans, SSRIs, other SNRIs, linezolid (an antibiotic which is a reversible non-selective MAOI), lithium, tramadol, or St. John's wort. If concomitant treatment with venlafaxine hydrochloride extended-release and these drugs is clinically warranted, careful observation of the patient is advised, particularly during treatment initiation and dose increases. The concomitant use of venlafaxine hydrochloride extended-release with tryptophan supplements is not recommended [ see Dosage and Administration (2.9), Contraindications (4.2), and Warnings and Precautions (5.2)].

7.4 Drugs that Interfere with Hemostasis (e.g., NSAIDs, Aspirin, and Warfarin)

Serotonin release by platelets plays an important role in hemostasis. The use of psychotropic drugs that interfere with serotonin reuptake is associated with the occurrence of upper gastrointestinal bleeding and concurrent use of an NSAID or aspirin may potentiate this risk of bleeding [ see Warnings and Precautions (5.4)]. Altered anticoagulant effects, including increased bleeding, have been reported when SSRIs and SNRIs are coadministered with warfarin. Patients receiving warfarin therapy should be carefully monitored when venlafaxine hydrochloride extended-release is initiated or discontinued.

7.5 Weight Loss Agents

The safety and efficacy of venlafaxine therapy in combination with weight loss agents, including phentermine, have not been established. Coadministration of venlafaxine hydrochloride extended-release and weight loss agents is not recommended. Venlafaxine hydrochloride extended-release is not indicated for weight loss alone or in combination with other products.

7.6 Effects of Other Drugs on Venlafaxine hydrochloride Extended-Release

Figure 1: Effect of interacting drugs on the pharmacokinetics of venlafaxine and active metabolite O-desmethylvenlafaxine (ODV).

Abbreviations: ODV, O-desmethylvenlafaxine; AUC, area under the curve; Cmax, peak plasma concentrations; EM's, extensive metabolizers; PM's, poor metabolizers

* No dose adjustment on co-administration with CYP2D6 inhibitors (Fig 3 and Metabolism Section 12.3)

7.7 Effects of Venlafaxine hydrochloride Extended-Release on Other Drugs

Figure 2: Effect of venlafaxine on the pharmacokinetics interacting drugs and their active metabolites.

Abbreviations: AUC, area under the curve; Cmax, peak plasma concentrations; OH, hydroxyl

* Data for 2-OH desipramine were not plotted to enhance clarity; the fold change and 90% CI for Cmax and AUC of 2-OH desipramine were 6.6 (5.5, 7.9) and 4.4 (3.8, 5.0), respectively.

Note:
*: Administration of venlafaxine in a stable regimen did not exaggerate the psychomotor and psychometric effects induced by ethanol in these same subjects when they were not receiving venlafaxine.

7.8 Drug-Laboratory Test Interactions

False-positive urine immunoassay screening tests for phencyclidine (PCP) and amphetamine have been reported in patients taking venlafaxine. This is due to lack of specificity of the screening tests. False positive test results may be expected for several days following discontinuation of venlafaxine therapy. Confirmatory tests, such as gas chromatography/mass spectrometry, will distinguish venlafaxine from PCP and amphetamine.

8 USE IN SPECIFIC POPULATIONS

8.1 Pregnancy

Teratogenic Effects – Pregnancy Category C

Venlafaxine did not cause malformations in offspring of rats or rabbits given doses up to 2.5 times (rat) or 4 times (rabbit) the maximum recommended human daily dose on a mg/m^2 basis. However, in rats, there was a decrease in pup weight, an increase in stillborn pups, and an increase in pup deaths during the first 5 days of lactation, when dosing began during pregnancy and continued until weaning. The cause of these deaths is not known. These effects occurred at 2.5 times (mg/m^2) the maximum human daily dose. The no effect dose for rat pup mortality was 0.25 times the human dose on a mg/m^2 basis. In reproductive developmental studies in rats and rabbits with O-desmethylvenlafaxine (ODV), the major human metabolite of venlafaxine, evidence of teratogenicity was not observed at exposure margins of 13 in rats and 0.3 in rabbits. There are no adequate and well-controlled studies in pregnant women. Venlafaxine hydrochloride extended-release should be used during pregnancy only if the potential benefit justifies the potential risk to the fetus. Because animal reproduction studies are not always predictive of human response, this drug should be used during pregnancy only if clearly needed.

Non-teratogenic Effects

Neonates exposed to venlafaxine hydrochloride extended-release, other SNRIs, or SSRIs, late in the third trimester have developed complications requiring prolonged hospitalization, respiratory support, and tube feeding. Such complications can arise immediately upon delivery. Reported clinical findings have included respiratory distress, cyanosis, apnea, seizures, temperature instability, feeding difficulty, vomiting, hypoglycemia, hypotonia, hypertonia, hyperreflexia, tremor, jitteriness, irritability, and constant crying. These features are consistent with either a direct toxic effect of SSRIs and SNRIs, or possibly a drug discontinuation syndrome. It should be noted, that in some cases the clinical picture is consistent with serotonin syndrome [ see Warnings and Precautions (5.2) and Drug Interactions (7.3)]. When treating a pregnant woman with venlafaxine hydrochloride extended-release during the third trimester, the physician should carefully consider the potential risks and benefits of treatment.

8.2 Labor and Delivery

The effect of venlafaxine on labor and delivery in humans is unknown.

8.3 Nursing Mothers

Venlafaxine and ODV have been reported to be excreted in human milk. Because of the potential for serious adverse reactions in nursing infants from venlafaxine hydrochloride extended-release, a decision should be made whether to discontinue nursing or to discontinue the drug, taking into account the importance of the drug to the mother.

8.4 Pediatric Use

Two placebo-controlled trials in 766 pediatric patients with MDD and two placebo-controlled trials in 793 pediatric patients with GAD have been conducted with venlafaxine hydrochloride extended-release, and the data were not sufficient to support a claim for use in pediatric patients.

Anyone considering the use of venlafaxine hydrochloride extended-release in a child or adolescent must balance the potential risks with the clinical need [ see Boxed Warning, Warnings and Precautions (5.1, 5.10, 5.11) and Adverse Reactions (6.4)].

Although no studies have been designed to primarily assess venlafaxine hydrochloride extended-release impact on the growth, development, and maturation of children and adolescents, the studies that have been done suggest that venlafaxine hydrochloride extended-release may adversely affect weight and height (see Warnings and Precautions (5.10)). Should the decision be made to treat a pediatric patient with venlafaxine hydrochloride extended-release, regular monitoring of weight and height is recommended during treatment, particularly if treatment is to be continued long-term [ see Warnings and Precautions (5.10, 5.11)]. The safety of venlafaxine hydrochloride extended-release treatment for pediatric patients has not been systematically assessed for chronic treatment longer than six months in duration. In the studies conducted in pediatric patients (ages 6–17), the occurrence of blood pressure and cholesterol increases considered to be clinically relevant in pediatric patients was similar to that observed in adult patients. Consequently, the precautions for adults apply to pediatric patients [ see Warnings and Precautions (5.3, 6.3)].

8.5 Geriatric Use

The percentage of patients in clinical studies for venlafaxine hydrochloride extended-release for MDD, GAD, SAD, and PD who were 65 years of age or older are shown in Table 15.

Table 15: Percentage (and Number of Patients Studied) of Patients 65 Years of Age and Older by Indication [In addition, in the premarketing assessment of venlafaxine hydrochloride immediate-release, 12% (357/2,897) of patients were ≥ 65 years of age.]
Indication | Venlafaxine hydrochloride Extended-Release
MDD | 4 (14/357)
GAD | 6 (77/1,381)
SAD | 1 (10/819)
PD | 2 (16/1,001)

No overall differences in effectiveness or safety were observed between geriatric patients and younger patients, and other reported clinical experience generally has not identified differences in response between the elderly and younger patients. However, greater sensitivity of some older individuals cannot be ruled out. SSRIs and SNRIs, including venlafaxine hydrochloride extended-release, have been associated with cases of clinically significant hyponatremia in elderly patients, who may be at greater risk for this adverse event [ see Warnings and Precautions (5.9)].

The pharmacokinetics of venlafaxine and ODV are not substantially altered in the elderly [ see Clinical Pharmacology (12.3) and (see Figure 3)]. No dose adjustment is recommended for the elderly on the basis of age alone, although other clinical circumstances, some of which may be more common in the elderly, such as renal or hepatic impairment, may warrant a dose reduction [ see Dosage and Administration (2.6)].

8.6 Age and Gender

A population pharmacokinetic analysis of 404 venlafaxine hydrochloride immediate-release treated patients from two studies involving both twice daily and three times daily regimens showed that dose-normalized trough plasma levels of either venlafaxine or ODV were unaltered by age or gender differences. Dosage adjustment based on the age or gender of a patient is generally not necessary [ see Dosage and Administration (2.6)] (see Table 15).

8.7 Use in Patient Subgroups

Figure 3: Pharmacokinetics of venlafaxine and its metabolite O-desmethylvenlafaxine (ODV) in special populations.

Abbreviations: ODV, O-desmethylvenlafaxine; AUC, area under the curve; Cmax, peak plasma concentrations;
*Similar effect is expected with strong CYP2D6 inhibitors

9 DRUG ABUSE AND DEPENDENCE

9.1 Controlled Substance

Venlafaxine hydrochloride extended-release is not a controlled substance.

9.2 Abuse

While venlafaxine has not been systematically studied in clinical studies for its potential for abuse, there was no indication of drug-seeking behavior in the clinical studies. However, it is not possible to predict on the basis of premarketing experience the extent to which a CNS-active drug will be misused, diverted, and/or abused once marketed. Consequently, physicians should carefully evaluate patients for history of drug abuse and follow such patients closely, observing them for signs of misuse or abuse of venlafaxine (e.g., development of tolerance, incrementation of dose, drug-seeking behavior).

9.3 Dependence

In vitro studies revealed that venlafaxine has virtually no affinity for opiate, benzodiazepine, phencyclidine (PCP), or N-methyl-D-aspartic acid (NMDA) receptors.

Venlafaxine was not found to have any significant CNS stimulant activity in rodents. In primate drug discrimination studies, venlafaxine showed no significant stimulant or depressant abuse liability.

Discontinuation effects have been reported in patients receiving venlafaxine [ see Dosage and Administration (2.8)].

10 OVERDOSAGE

10.1 Human Experience

During the premarketing evaluations of venlafaxine hydrochloride extended-release (for MDD, GAD, SAD, and PD) and venlafaxine hydrochloride immediate-release (for MDD), there were twenty reports of acute overdosage with venlafaxine (6 and 14 reports in venlafaxine hydrochloride extended-release and venlafaxine hydrochloride immediate-release patients, respectively), either alone or in combination with other drugs and/or alcohol.

Somnolence was the most commonly reported symptom. Among the other reported symptoms were paresthesia of all four limbs, moderate dizziness, nausea, numb hands and feet, and hot-cold spells 5 days after the overdose. In most cases, no signs or symptoms were associated with overdose. The majority of the reports involved ingestion in which the total dose of venlafaxine taken was estimated to be no more than several-fold higher than the usual therapeutic dose. One patient who ingested 2.75 g of venlafaxine was observed to have two generalized convulsions and a prolongation of QTc to 500 msec, compared with 405 msec at baseline. Mild sinus tachycardia was reported in two of the other patients.

Actions taken to treat the overdose included no treatment, hospitalization and symptomatic treatment, and hospitalization plus treatment with activated charcoal. All patients recovered.

In postmarketing experience, overdose with venlafaxine has occurred predominantly in combination with alcohol and/or other drugs. The most commonly reported events in overdosage include tachycardia, changes in level of consciousness (ranging from somnolence to coma), mydriasis, seizures, and vomiting. Electrocardiogram changes (e.g., prolongation of QT interval, bundle branch block, QRS prolongation), ventricular tachycardia, bradycardia, hypotension, rhabdomyolysis, vertigo, liver necrosis, serotonin syndrome, and death have been reported.

Published retrospective studies report that venlafaxine overdosage may be associated with an increased risk of fatal outcomes compared to that observed with SSRI antidepressant products, but lower than that for tricyclic antidepressants. Epidemiological studies have shown that venlafaxine-treated patients have a higher preexisting burden of suicide risk factors than SSRI-treated patients. The extent to which the finding of an increased risk of fatal outcomes can be attributed to the toxicity of venlafaxine in overdosage, as opposed to some characteristic(s) of venlafaxine-treated patients, is not clear. Prescriptions for venlafaxine hydrochloride extended-release should be written for the smallest quantity of capsules consistent with good patient management, in order to reduce the risk of overdose.

10.2 Management of Overdosage

Consult a Certified Poison Control Center for up-to-date guidance and advice (1-800-222-1222 or Poison Center). In case of an overdose, provide supportive care, including close medical supervision and monitoring. Treatment should consist of those general measures employed in the management of overdosage with any drug. Consider the possibility of multiple drug overdose. Ensure an adequate airway, oxygenation, and ventilation. Monitor cardiac rhythm and vital signs. Provide supportive and symptomatic measures.

11 DESCRIPTION

Venlafaxine hydrochloride extended-release capsules are for once-a-day oral administration and contains venlafaxine hydrochloride, a serotonin and norepinephrine reuptake inhibitor (SNRI).

Venlafaxine is designated (R/S)-1-[2-(dimethylamino)-1-(4-methoxyphenyl)ethyl] cyclohexanol hydrochloride or (±)-1-[α- [(dimethylamino)methyl]-p-methoxybenzyl] cyclohexanol hydrochloride and has the empirical formula of C17H27NO2 HCl. Its molecular weight is 313.86. The structural formula is shown as follows:

Venlafaxine hydrochloride is a white to off-white crystalline solid, with a solubility of 572 mg/mL in water (adjusted to ionic strength of 0.2 M with sodium chloride). Its octanol:water (0.2 M sodium chloride) partition coefficient is 0.43.

Drug release is controlled by diffusion through the coating membrane on the spheroids and is not pH-dependent. Capsules contain venlafaxine hydrochloride equivalent to 37.5 mg, 75 mg, or 150 mg venlafaxine. Inactive ingredients consist of cellulose, ethylcellulose, gelatin, hypromellose, iron oxide, and titanium dioxide.

12 CLINICAL PHARMACOLOGY

12.1 Mechanism of Action

The exact mechanism of the antidepressant action of venlafaxine in humans is unknown, but is thought to be related to the potentiation of serotonin and norepinephrine in the central nervous system, through inhibition of their reuptake. Non- clinical studies have demonstrated that venlafaxine and its active metabolite, ODV, are potent and selective inhibitors of neuronal serotonin and norepinephrine reuptake and weak inhibitors of dopamine reuptake.

12.2 Pharmacodynamics

Venlafaxine and ODV have no significant affinity for muscarinic-cholinergic, H1-histaminergic, or α1-adrenergic receptors in vitro. Pharmacologic activity at these receptors is hypothesized to be associated with the various anticholinergic, sedative, and cardiovascular effects seen with other psychotropic drugs. Venlafaxine and ODV do not possess monoamine oxidase (MAO) inhibitory activity.

12.3 Pharmacokinetics

Steady-state concentrations of venlafaxine and ODV in plasma are attained within 3 days of oral multiple-dose therapy. Venlafaxine and ODV exhibited linear kinetics over the dose range of 75 to 450 mg per day. Mean±SD steady-state plasma clearance of venlafaxine and ODV is 1.3±0.6 and 0.4±0.2 L/h/kg, respectively; apparent elimination half-life is 5±2 and 11±2 hours, respectively; and apparent (steady-state) volume of distribution is 7.5±3.7 and 5.7±1.8 L/kg, respectively. Venlafaxine and ODV are minimally bound at therapeutic concentrations to plasma proteins (27% and 30%, respectively).

Absorption and Distribution

Venlafaxine is well absorbed and extensively metabolized in the liver. ODV is the major active metabolite. On the basis of mass balance studies, at least 92% of a single oral dose of venlafaxine is absorbed. The absolute bioavailability of venlafaxine is approximately 45%.

Administration of venlafaxine hydrochloride extended-release (150 mg once daily) generally resulted in lower Cmax and later Tmax values than for venlafaxine hydrochloride immediate-release administered twice daily (Table 16). When equal daily doses of venlafaxine were administered as either an immediate-release tablet or the extended-release capsule, the exposure to both venlafaxine and ODV was similar for the two treatments, and the fluctuation in plasma concentrations was slightly lower with the venlafaxine hydrochloride extended-release capsule. Therefore, venlafaxine hydrochloride extended-release provides a slower rate of absorption, but the same extent of absorption compared with the immediate-release tablet.

Table 16: Comparison of Cmax and Tmax Values for Venlafaxine and ODV Following Oral Administration of Venlafaxine hydrochloride Extended-Release and Venlafaxine hydrochloride Immediate-Release)
 | Venlafaxine |  | ODV
 | Cmax (ng/mL) | Tmax (h) | Cmax (ng/mL) | Tmax (h)
Venlafaxine hydrochloride Extended-Release (150 mg once daily) | 150 | 5.5 | 260 | 9
Venlafaxine hydrochloride Immediate-Release (75 mg twice daily) | 225 | 2 | 290 | 3

Food did not affect the bioavailability of venlafaxine or its active metabolite, ODV. Time of administration (AM versus PM) did not affect the pharmacokinetics of venlafaxine and ODV from the 75 mg venlafaxine hydrochloride extended-release capsule.

Venlafaxine is not highly bound to plasma proteins; therefore, administration of venlafaxine hydrochloride extended-release to a patient taking another drug that is highly protein-bound should not cause increased free concentrations of the other drug.

Metabolism and Elimination

Following absorption, venlafaxine undergoes extensive presystemic metabolism in the liver, primarily to ODV, but also to N-desmethylvenlafaxine, N,O-didesmethylvenlafaxine, and other minor metabolites. In vitro studies indicate that the formation of ODV is catalyzed by CYP2D6; this has been confirmed in a clinical study showing that patients with low CYP2D6 levels (poor metabolizers) had increased levels of venlafaxine and reduced levels of ODV compared to people with normal CYP2D6 levels (extensive metabolizers) [ see Use in Specific Populations (8.7)].

Approximately 87% of a venlafaxine dose is recovered in the urine within 48 hours as unchanged venlafaxine (5%), unconjugated ODV (29%), conjugated ODV (26%), or other minor inactive metabolites (27%). Renal elimination of venlafaxine and its metabolites is thus the primary route of excretion.

13 NONCLINICAL TOXICOLOGY

13.1 Carcinogenesis, Mutagenesis, Impairment of Fertility

Carcinogenesis

Tumors were not increased by venlafaxine treatment in mice or rats. Venlafaxine was given by oral gavage to mice for 18 months at doses up to 120 mg/kg per day, which was 1.7 times the maximum recommended human dose on a mg/m^2 basis. Venlafaxine was also given to rats by oral gavage for 24 months at doses up to 120 mg/kg per day. In rats receiving the 120 mg/kg dose, plasma concentrations of venlafaxine at necropsy were 1 times (male rats) and 6 times (female rats) the plasma concentrations of patients receiving the maximum recommended human dose. Plasma levels of the O-desmethyl metabolite (ODV) were lower in rats than in patients receiving the maximum recommended dose. O-desmethylvenlafaxine (ODV), the major human metabolite of venlafaxine, administered by oral gavage to mice and rats for 2 years did not increase the incidence of tumors in either study. Mice received ODV at dosages up to 500/300 mg/kg/day (dosage lowered after 45 weeks of dosing). The exposure at the 300 mg/kg/day dose is 9 times that of a human dose of 225 mg/day. Rats received ODV at dosages up to 300 mg/kg/day (males) or 500 mg/kg/day (females). The exposure at the highest dose is approximately 8 (males) or 11 (females) times that of a human dose of 225 mg/day.

Mutagenesis

Venlafaxine and the major human metabolite, ODV, were not mutagenic in the Ames reverse mutation assay in Salmonella bacteria or the Chinese hamster ovary/HGPRT mammalian cell forward gene mutation assay. Venlafaxine was also not mutagenic or clastogenic in the in vitro BALB/c-3T3 mouse cell transformation assay, the sister chromatid exchange assay in cultured Chinese hamster ovary cells, or in the in vivo chromosomal aberration assay in rat bone marrow. ODV was not clastogenic in the in vitro Chinese hamster ovary cell chromosomal aberration assay or in the in vivo chromosomal aberration assay in rats.

Impairment of Fertility

Reproduction and fertility studies of venlafaxine in rats showed no adverse effects of venlafaxine on male or female fertility at oral doses of up to 2 times the maximum recommended human dose of 225 mg/day on a mg/m^2 basis. However, reduced fertility was observed in a study in which male and female rats were treated with O-desmethylvenlafaxine (ODV), the major human metabolite of venlafaxine, prior to and during mating and gestation. This occurred at an ODV exposure (AUC) approximately 2 to 3 times that associated with a human venlafaxine dose of 225 mg/day.

14 CLINICAL STUDIES

14.1 Major Depressive Disorder

The efficacy of venlafaxine hydrochloride extended-release capsules as a treatment for Major Depressive Disorder (MDD) was established in two placebo-controlled, short-term (8 weeks for study 1; 12 weeks for study 2), flexible-dose studies, with doses starting at 75 mg per day and ranging to 225 mg per day in adult outpatients meeting DSM-III-R or DSM-IV criteria for MDD. In moderately depressed outpatients, the initial dose of venlafaxine was 75 mg per day. In both studies, venlafaxine hydrochloride extended-release demonstrated superiority over placebo on the primary efficacy measure defined as change from baseline in the HAM-D-21 total score to the endpoint visit, venlafaxine hydrochloride extended-release also demonstrated superiority over placebo on the key secondary efficacy endpoint, the Clinical Global Impressions (CGI) Severity of Illness scale. Examination of gender subsets of the population studied did not reveal any differential responsiveness on the basis of gender.

A 4-week study of inpatients meeting DSM-III-R criteria for MDD with melancholia utilizing venlafaxine hydrochloride immediate-release in a range of 150 to 375 mg per day (divided in a three-times-a-day schedule) demonstrated superiority of venlafaxine hydrochloride immediate-release over placebo based on the HAM-D-21 total score. The mean dose in completers was 350 mg per day (study 3).

In a longer-term study, adult outpatients with MDD who had responded during an 8-week open-label study on venlafaxine hydrochloride extended-release (75, 150, or 225 mg, once daily every morning) were randomized to continuation of their same venlafaxine hydrochloride extended-release dose or to placebo, for up to 26 weeks of observation for relapse. Response during the open-label phase was defined as a CGI Severity of Illness item score of ≤3 and a HAM-D-21 total score of ≤10 at the day 56 evaluation. Relapse during the double-blind phase was defined as follows: (1) a reappearance of major depressive disorder as defined by DSM-IV criteria and a CGI Severity of Illness item score of ≥4 (moderately ill), (2) 2 consecutive CGI Severity of Illness item scores of ≥4, or (3) a final CGI Severity of Illness item score of ≥4 for any patient who withdrew from the study for any reason. Patients receiving continued venlafaxine hydrochloride extended-release treatment experienced statistically significantly lower relapse rates over the subsequent 26 weeks compared with those receiving placebo (study 4).

In a second longer term trial, adult outpatients with MDD, recurrent type, who had responded (HAM-D-21 total score ≤ 12 at the day 56 evaluation) and continued to be improved [defined as the following criteria being met for days 56 through 180: (1) no HAM-D-21 total score ≥ 20; (2) no more than 2 HAM-D-21 total scores > 10, and (3) no single CGI Severity of Illness item score ≥ 4 (moderately ill)] during an initial 26 weeks of treatment on venlafaxine hydrochloride immediate-release [100 to 200 mg per day, on a twice daily schedule] were randomized to continuation of their same venlafaxine hydrochloride immediate-release dose or to placebo. The follow-up period to observe patients for relapse, defined as a CGI Severity of Illness item score ≥ 4, was for up to 52 weeks. Patients receiving continued venlafaxine hydrochloride immediate-release treatment experienced statistically significantly lower relapse rates over the subsequent 52 weeks compared with those receiving placebo (study 5).

Table 17: Major Depressive Disorder Studies:
Study number | Treatment Group |  | Primary Efficacy Measure: HAM-D Score
 |  | MeanBaseline Score (SD) | LSMean Changefrom Baseline | Placebo SubtractedDifference [Difference (drug minus placebo) in least-squares mean change from baseline] (95%CI)
Study 1 | Venlafaxine hydrochloride Extended-Release (75–225 mg/day) [Doses statistically significantly superior to placebo.] | 24.5 | -11.7 | -4.45(-6.66,-2.25)
Study 1 | Placebo | 23.6 | -7.24 | -
Study 2 | Venlafaxine hydrochloride Extended-Release (75–225 mg/day) | 24.5 | -15.11 | -6.40(-8.45,-4.34)
Study 2 | Placebo | 24.9 | -8.71
Study 3 | Venlafaxine hydrochloride Immediate-Release (150–375 mg/day) | 28.2 (0.5) | -14.9 | -10.2 (-14.4,-6.0)
Study 3 | Placebo | 28.6 (0.6) | -4.7 | -
SD: standard deviation; LS Mean: least-squares mean; CI: confidence interval.

14.2 Generalized Anxiety Disorder

The efficacy of venlafaxine hydrochloride extended-release as a treatment for Generalized Anxiety Disorder (GAD) was established in two 8-week, placebo-controlled, fixed-dose studies (75 to 225 mg per day), one 6-month, placebo-controlled, flexible-dose study (75 to 225 mg per day), and one 6-month, placebo-controlled, fixed-dose study (37.5, 75, and 150 mg per day) in adult outpatients meeting DSM-IV criteria for GAD.

In one 8-week study, venlafaxine hydrochloride extended-release demonstrated superiority over placebo for the 75, 150, and 225 mg per day doses as measured by the Hamilton Rating Scale for Anxiety (HAM-A) total score, both the HAM-A anxiety and tension items, and the Clinical Global Impressions (CGI) scale. However, the 75 and 150 mg per day doses were not as consistently effective as the highest dose (study 1). A second 8-week study evaluating doses of 75 and 150 mg per day and placebo showed that both doses were more effective than placebo on some of these same outcomes; however, the 75 mg per day dose was more consistently effective than the 150 mg per day dose (study 2). A dose-response relationship for effectiveness in GAD was not clearly established in the 75 to 225 mg per day dose range studied.

Two 6-month studies, one evaluating venlafaxine hydrochloride extended-release doses of 37.5, 75, and 150 mg per day (study 3) and the other evaluating venlafaxine hydrochloride extended-release doses of 75 to 225 mg per day (study 4), showed that daily doses of 75 mg or higher were more effective than placebo on the HAM-A total, both the HAM-A anxiety and tension items, and the CGI scale during 6 months of treatment. While there was also evidence for superiority over placebo for the 37.5 mg per day dose, this dose was not as consistently effective as the higher doses.

Examination of gender subsets of the population studied did not reveal any differential responsiveness on the basis of gender.

Table 18: Generalized Anxiety Disorder Studies:
Study Number | Treatment Group | Primary Efficacy Measure: HAM-A Score
 |  | Mean Baseline Score (SD) | LS Mean Change from Baseline (SE) | Placebo Subtracted Difference [Difference (drug minus placebo) in least-squares mean change from baseline] (95% CI)
Study 1 | Ven XR 75 mg | 24.7 | -11.1 (0.95) | -1.5 (-3.8, 0.8)
Study 1 | Ven XR 150 mg | 24.5 | -11.7 (0.87) | -2.2 (-4.5, 0.1)
Study 1 | Ven XR 225 mg | 23.6 | -12,1 (0.81) | -2.6 (-4.9, -0.3)
Study 1 | Placebo | 24.1 | -9.5 (0.85)
Study 2 | Ven XR 75 mg | 23.7 | -10.6 (0.82) | -2.6 (-4.6, -0.5)
Study 2 | Ven XR 150 mg | 23.0 | -9.8 (0.86) | -1.7 (-3.8, 0.3)
Study 2 | Placebo | 23.7 | -8.0 (0.73)
Study 3 | Ven XR 37.5 mg | 26.6 (0.4) | -13.8 | -2.8 (-5.1, -0.6)
Study 3 | Ven XR 75 mg | 26.3 (0.4) | -15.5 | -4.6 (-6.9, -2.3)
Study 3 | Ven XR150 mg | 26.3 (0.4) | -16.4 | -5.5 (-7.8, -3.1)
Study 3 | Placebo | 26.7 (0.5) | -11.0
Study 4 | Ven XR 75–225 mg | 25.0 | -13.4 (0.79) | - 4.7 (-6.6, -2.9)
Study 4 | Placebo | 24.9 | -8.7 (0.70)
SD: standard deviation; SE: standard error; LS Mean: least-squares mean; CI: confidence interval.
* Doses statistically significantly superior to placebo.

14.3 Social Anxiety Disorder (also known as Social Phobia)

The efficacy of venlafaxine hydrochloride extended-release as a treatment for Social Anxiety Disorder (SAD) was established in four double-blind, parallel-group, 12-week, multicenter, placebo-controlled, flexible-dose studies (studies 1–4) and one double-blind, parallel-group, 6-month, placebo-controlled, fixed/flexible-dose study, which included doses in a range of 75 to 225 mg per day in adult outpatients meeting DSM-IV criteria for SAD (study 5).

In these five studies, venlafaxine hydrochloride extended-release was statistically significantly more effective than placebo on change from baseline to endpoint on the Liebowitz Social Anxiety Scale (LSAS) total score. There was no evidence for any greater effectiveness of the 150 to 225 mg per day group compared to the 75 mg per day group in the 6-month study.

Examination of subsets of the population studied did not reveal any differential responsiveness on the basis of gender. There was insufficient information to determine the effect of age or race on outcome in these studies.

Table 19: Social Anxiety Disorder Studies:
Study Number | Treatment Group | Primary Efficacy Measure: LSAS Score
 |  | Mean Baseline Score (SD) | LS Mean Change from Baseline (SE) | Placebo Subtracted Difference [Difference (drug minus placebo) in least-squares mean change from baseline] (95% CI)
Study 1 | Ven XR (75–225 mg) | 91.1 | -31.0(2.22) | 11.2 (-5.3, -17.1)
Study 1 | Placebo | 86.7 | -19.9 (2.22) | -
Study 2 | Ven XR (75–225 MG) | 90.8 | -32.8 (2.69) | -10.7 (-3.7,-17.6)
Study 2 | Placebo | 87.4 | -22.1 (2.66) | -
Study 3 | Ven XR (75–225 MG) | 83.2 | -36.0 (2.35) | -16.9(-22.6, -11.2)
Study 3 | Placebo | 83.6 | -19.1 (2.40) | -12.7 (-6.5, -19.0)
Study 4 | Ven XR (75–225 mg) | 86.2 | -35.0 (2.64) | -14.6 (-21.8, -7.4)
Study 4 | Placebo | 86.1 | -22.2 (2,47)
Study 5 | Ven XR 75 mg | 91.8 | -38.1 (3.16) | -14.6 (-21.8, -7.4)
Study 5 | Ven XR (150–225 mg) | 86.2 | -37.6 (3.05) | -14.1 (-21.3, -6.9)
Study 5 | Placebo | 89.3 | -23.5 (3.08)
SD: standard deviation; SE: standard error; LS Mean: least-squares mean; CI: confidence interval.
* Doses statistically significantly superior to placebo.

14.4 Panic Disorder

The efficacy of venlafaxine hydrochloride extended-release as a treatment for Panic Disorder (PD) was established in two double-blind, 12-week, multicenter, placebo-controlled studies in adult outpatients meeting DSM-IV criteria for PD, with or without agoraphobia. Patients received fixed doses of 75 or 150 mg per day in one study (study 1) and 75 or 225 mg per day in the other study (study 2).

Efficacy was assessed on the basis of outcomes in three variables: (1) percentage of patients free of full-symptom panic attacks on the Panic and Anticipatory Anxiety Scale (PAAS); (2) mean change from baseline to endpoint on the Panic Disorder Severity Scale (PDSS) total score; and (3) percentage of patients rated as responders (much improved or very much improved) on the Clinical Global Impressions (CGI) Improvement scale. In these two studies, venlafaxine hydrochloride extended-release was statistically significantly more effective than placebo (for each fixed dose) on all three endpoints, but a dose-response relationship was not clearly established.

Examination of subsets of the population studied did not reveal any differential responsiveness on the basis of gender. There was insufficient information to determine the effect of age or race on outcome in these studies.

In a longer term study (study 3), adult outpatients meeting DSM-IV criteria for PD who had responded during a 12-week open phase with venlafaxine hydrochloride extended-release (75 to 225 mg per day) were randomly assigned to continue the same venlafaxine hydrochloride extended-release dose (75, 150, or 225 mg) or switch to placebo for observation for relapse under double-blind conditions. Response during the open phase was defined as ≤ 1 full-symptom panic attack per week during the last 2 weeks of the open phase and a CGI Improvement score of 1 (very much improved) or 2 (much improved). Relapse during the double-blind phase was defined as having 2 or more full-symptom panic attacks per week for 2 consecutive weeks or having discontinued due to loss of effectiveness as determined by the investigators during the study. Randomized patients were in response status for a mean time of 34 days prior to being randomized. In the randomized phase following the 12-week open-label period, patients receiving continued venlafaxine hydrochloride extended-release experienced a statistically significantly longer time to relapse.

Table 20: Panic Disorder Studies:
Study Number | Treatment Group | Primary Efficacy Measure: Whether Free of Full-symptom Panic Attacks
 |  | Percent of patients Free of Full symptom panic attack | Adjusted Odds Ratio [Odds ratio (drug to placebo) in terms of probability of free of full-symptom panic attacks based on logistic regression model.] to placebo | Adjusted Odds Ratio 95% Confidence Interval
Study 1 | Ven XR 75 mg [Doses statistically significantly superior to placebo.] | 54.1% (85/157) | 2. 268 | (1.43, 3.59)
Study 1 | Ven XR 150 mg | 61.4% (97/158) | 3.035 | (1.91, 4.82)
Study 1 | Placebo | 34.4% (53/154) | -- | --
Study 2 | Ven XR 75 mg | 64.1% (100/156) | 2.350 | (1.46, 3.78)
Study 2 | Ven XR 225 mg | 70.0% (112/160) | 2.890 | (1.80, 4.64)
Study 2 | Placebo | 46.5% (73/157) | -- | --
95%CI: 95% confidence interval without adjusting for multiple dose arms.

14.5 Pediatric Patients

Two placebo-controlled studies in 766 pediatric patients with MDD and two placebo-controlled studies in 793 pediatric patients with GAD have been conducted with venlafaxine hydrochloride extended-release, and the data were not sufficient to support a claim for use in pediatric patients.

16 HOW SUPPLIED/STORAGE AND HANDLING

Venlafaxine hydrochloride extended-release capsules are available as follows:

- 37.5 mg, grey cap/peach body with " W" and "Effexor XR" on the cap and "37.5" on the body.
  NDC 60505-3778-3, bottle of 30 capsules in unit-of-use package.
  NDC 60505-3778-9, bottle of 90 capsules in unit-of-use package.
- 75 mg, peach cap and body with " W" and "Effexor XR" on the cap and "75" on the body.
  NDC 60505-3779-3, bottle of 30 capsules in unit-of-use package.
  NDC 60505-3779-9, bottle of 90 capsules in unit-of-use package.
- 150 mg, dark orange cap and body with " W" and "Effexor XR" on the cap and "150" on the body.
  NDC 60505-3780-3, bottle of 30 capsules in unit-of-use package.
  NDC 60505-3780-9, bottle of 90 capsules in unit-of-use package.

STORAGE AND HANDLING

Store at controlled room temperature, 20° to 25°C (68° to 77°F).

The unit-of-use package is intended to be dispensed as a unit.

17 PATIENT COUNSELING INFORMATION

See FDA-approved patient labeling (Medication Guide).

Prescribers or other healthcare professionals should inform patients, their families, and their caregivers about the benefits and risks associated with treatment with venlafaxine hydrochloride extended-release and should counsel them in its appropriate use. A patient Medication Guide about "Antidepressant Medicines, Depression and Other Serious Mental Illnesses, and Suicidal Thoughts or Actions" is available for venlafaxine hydrochloride extended-release. The prescriber or healthcare professional should instruct patients, their families, and their caregivers to read the Medication Guide and should assist them in understanding its contents. Patients should be given the opportunity to discuss the contents of the Medication Guide and to obtain answers to any questions they may have. The complete text of the Medication Guide is reprinted at the end of this document.

Patients should be advised of the following issues and should be asked to alert their prescriber if these occur while taking venlafaxine hydrochloride extended-release.

Suicidal Thoughts and Behaviors

Advise patients, their families and caregivers to look for the emergence of suicidality, worsening of depression, and other psychiatric symptoms (anxiety, agitation, panic attacks, insomnia, irritability, hostility, aggressiveness, impulsivity, akathisia, psychomotor restlessness, hypomania, mania, other unusual changes in behavior), especially early during treatment and when the dose is adjusted up or down. Such symptoms should be reported to the patient's prescriber or health professional, especially if they are severe, abrupt in onset, or were not part of the patient's presenting symptoms. Symptoms such as these may be associated with an increased risk for suicidal thinking and behavior and indicate a need for very close monitoring [ see Boxed Warning and Warnings and Precautions (5.1)].

Concomitant Medication

Advise patients taking venlafaxine hydrochloride extended-release not to use concomitantly other products containing venlafaxine or desvenlafaxine. Healthcare professionals should instruct patients not to take venlafaxine hydrochloride extended-release with an MAOI or within 14 days of stopping an MAOI and to allow 7 days after stopping venlafaxine hydrochloride extended-release before starting an MAOI [ see Contraindications (4.2)].

Serotonin Syndrome

Patients should be cautioned about the risk of serotonin syndrome, with the concomitant use of venlafaxine hydrochloride extended-release and triptans, tramadol, tryptophan supplements, with antipsychotics or other dopamine antagonists, or other serotonergic agents [s ee Warnings and Precautions (5.2) and Drug Interactions (7.3)].

Elevated Blood Pressure

Advise patients that they should have regular monitoring of blood pressure when taking venlafaxine hydrochloride extended-release [ see Warnings and Precautions (5.3)].

Abnormal Bleeding

Patients should be cautioned about the concomitant use of venlafaxine hydrochloride extended-release and NSAIDs, aspirin, warfarin, or other drugs that affect coagulation since combined use of psychotropic drugs that interfere with serotonin reuptake and these agents has been associated with an increased risk of bleeding [ see Warnings and Precautions (5.4)].

Angle Closure Glaucoma

Patients should be advised that taking venlafaxine hydrochloride extended-release can cause mild pupillary dilation, which in susceptible individuals, can lead to an episode of angle closure glaucoma. Pre-existing glaucoma is almost always open-angle glaucoma because angle closure glaucoma, when diagnosed, can be treated definitively with iridectomy. Open-angle glaucoma is not a risk factor for angle closure glaucoma. Patients may wish to be examined to determine whether they are susceptible to angle closure, and have a prophylactic procedure (e.g., iridectomy), if they are susceptible [ see Warnings and Precautions (5.5)].

Activation of Mania/Hypomania

Advise patients, their families and caregivers to observe for signs of activation of mania/hypomania [ see Warnings and Precautions (5.6)].

Cardiovascular/Cerebrovascular Disease

Caution is advised in administering venlafaxine hydrochloride extended-release to patients with cardiovascular, cerebrovascular, or lipid metabolism disorders [ see Adverse Reactions (6.1)].

Serum Cholesterol and Triglyceride Elevation

Advise patients that elevations in total cholesterol, LDL and triglycerides may occur and that measurement of serum lipids may be considered [ see Warnings and Precautions (6.3)].

Discontinuation [Symptoms]

Advise patients not to stop taking venlafaxine hydrochloride extended-release without talking first with their healthcare professional. Patients should be aware that discontinuation effects may occur when stopping venlafaxine hydrochloride extended-release [ see Warnings and Precautions (5.7) and Adverse Reactions (6.1)].

Interference with Cognitive and Motor Performance

Caution patients about operating hazardous machinery, including automobiles, until they are reasonably certain that venlafaxine hydrochloride extended-release therapy does not adversely affect their ability to engage in such activities.

Alcohol

Advise patients to avoid alcohol while taking venlafaxine hydrochloride extended-release [ see Drug Interactions (7.6)].

Allergic Reactions

Advise patients to notify their physician if they develop allergic phenomena such as rash, hives, swelling, or difficulty breathing.

Pregnancy

Advise patients to notify their physician if they become pregnant or intend to become pregnant during therapy [ see Use in Specific Populations (8.1)].

Nursing

Advise patients to notify their physician if they are breast-feeding an infant [ see Use in Specific Populations (8.3)].

Residual Spheroids

Venlafaxine hydrochloride extended-release contains spheroids, which release the drug slowly into the digestive tract. The insoluble portion of these spheroids is eliminated, and patients may notice spheroids passing in the stool or via colostomy. Patients should be informed that the active medication has already been absorbed by the time the patient sees the spheroids.

Distributed by:

Apotex Corp.
Weston, Florida 33326

LAB-0501-16.0

Medication Guide

VENLAFAXINE XR
(venlafaxine hydrochloride)
(Extended-Release Capsules)

Read the Medication Guide that comes with venlafaxine hydrochloride extended-release capsules before you start taking it and each time you get a refill. There may be new information. This Medication Guide does not take the place of talking to your healthcare provider about your medical condition or treatment. Talk with your healthcare provider if there is something you do not understand or want to learn more about.

What is the most important information I should know about venlafaxine hydrochloride extended-release capsules?

Venlafaxine hydrochloride extended-release capsules and other antidepressant medicines may cause serious side effects, including:

- Suicidal thoughts or actions:
  - Venlafaxine hydrochloride extended-release capsules and other antidepressant medicines may increase suicidal thoughts or actions in some children, teenagers, or young adults within the first few months of treatment or when the dose is changed.
  - Depression or other serious mental illnesses are the most important causes of suicidal thoughts or actions.
  - Watch for these changes and call your healthcare provider right away if you notice:
    - New or sudden changes in mood, behavior, actions, thoughts, or feelings, especially if severe.
    - Pay particular attention to such changes when venlafaxine hydrochloride extended-release capsulesis started or when the dose is changed.
    Keep all follow-up visits with your healthcare provider and call between visits if you are worried about symptoms.
    Call your healthcare provider right away if you have any of the following symptoms, or call 911 if an emergency, especially if they are new, worse, or worry you:
    - attempts to commit suicide
    - acting on dangerous impulses
    - acting aggressive or violent
    - thoughts about suicide or dying
    - new or worse depression
    - new or worse anxiety or panic attacks
    - feeling agitated, restless, angry or irritable
    - trouble sleeping
    - an increase in activity or talking more than what is normal for you
    - other unusual changes in behavior or mood
    - Visual problems
      - eye pain
      - changes in vision
      - swelling or redness in or around the eye
      Only some people are at risk for these problems. You may want to undergo an eye examination to see if you are at risk and receive preventative treatment if you are.
  Call your healthcare provider right away if you have any of the following symptoms, or call 911 if an emergency. Venlafaxine hydrochloride extended-release capsules may be associated with these serious side effects:
- Serotonin Syndrome
  This condition can be life-threatening and may include :
  - agitation, hallucinations, coma or other changes in mental status
  - coordination problems or muscle twitching (overactive reflexes)
  - racing heartbeat, high or low blood pressure
  - sweating or fever
  - nausea, vomiting, or diarrhea
  - muscle rigidity
- Changes in blood pressure. venlafaxine hydrochloride extended-release capsules may:
  - increase your blood pressure. Control high blood pressure before starting treatment and monitor blood pressure regularly
- Enlarged pupils (mydriasis).
- Anxiety and insomnia.
- Changes in appetite or weight.
- Manic/hypomanic episodes:
  - greatly increased energy
  - severe trouble sleeping
  - racing thoughts
  - reckless behavior
  - unusually grand ideas
  - excessive happiness or irritability
  - talking more or faster than usual
- Low salt (sodium) levels in the blood. Elderly people may be at greater risk for this. Symptoms may include:
  - headache
  - weakness or feeling unsteady
  - confusion, problems concentrating or thinking or memory problems
- Seizures or convulsions.
- Abnormal bleeding: venlafaxine hydrochloride extended-release capsules and other antidepressant medicines may increase your risk of bleeding or bruising, especially if you take the blood thinner warfarin (Coumadin®, Jantoven®), a non-steroidal anti-inflammatory drug (NSAIDs, like ibuprofen or naproxen), or aspirin.
- Elevated cholesterol.
- Lung disease and pneumonia: venlafaxine hydrochloride extended-release capsules may cause rare lung problems. Symptoms include:
  - worsening shortness of breath
  - cough
  - chest discomfort
- Severe allergic reactions:
  - trouble breathing
  - swelling of the face, tongue, eyes or mouth
  - rash, itchy welts (hives) or blisters, alone or with fever or joint pain

Do not stop venlafaxine hydrochloride extended-release capsules without first talking to your healthcare provider. Stopping venlafaxine hydrochloride extended-release capsules too quickly or changing from another antidepressant too quickly may cause serious symptoms including:

- anxiety, irritability
- feeling tired, restless or problems sleeping
- headache, sweating, dizziness
- electric shock-like sensations, shaking, confusion, nightmares
- vomiting, nausea, diarrhea

What is venlafaxine hydrochloride extended-release capsules?

venlafaxine hydrochloride extended-release capsules is a prescription medicine used to treat depression. It is important to talk with your healthcare provider about the risks of treating depression and also the risks of not treating it. You should discuss all treatment choices with your healthcare provider. venlafaxine hydrochloride extended-release capsules is also used to treat:

- Generalized Anxiety Disorder (GAD)
- Social Anxiety Disorder (SAD)
- Panic Disorder (PD)

Talk to your healthcare provider if you do not think that your condition is getting better with venlafaxine hydrochloride extended-release capsules treatment.

Who should not take venlafaxine hydrochloride extended-release capsules?

Do not take venlafaxine hydrochloride extended-release capsules if you:

- are allergic to venlafaxine hydrochloride extended-release capsules or any of the ingredients in venlafaxine hydrochloride extended-release capsules. See the end of this Medication Guide for a complete list of ingredients in venlafaxine hydrochloride extended-release capsules.
- have uncontrolled angle-closure glaucoma
- take a Monoamine Oxidase Inhibitor (MAOI). Ask your healthcare provider or pharmacist if you are not sure if you take an MAOI, including the antibiotic linezolid.
  - Do not take an MAOI within 7 days of stopping venlafaxine hydrochloride extended-release capsules unless directed to do so by your physician.
  - Do not start venlafaxine hydrochloride extended-release capsulesif you stopped taking an MAOI in the last 2 weeks unless directed to do so by your physician.

People who take venlafaxine hydrochloride extended-release capsules close in time to an MAOI may have serious or even life-threatening side effects. Get medical help right away if you have any of these symptoms:

- high fever
- uncontrolled muscle spasms
- stiff muscles
- rapid changes in heart rate or blood pressure
- confusion
- loss of consciousness (pass out)

What should I tell my healthcare provider before taking venlafaxine hydrochloride extended-release capsules? Ask if you are not sure.

Before starting venlafaxine hydrochloride extended-release capsules, tell your healthcare provider if you:

- Are taking certain drugs such as:
  - Medicines used to treat migraine headaches such as:
    - triptans
  - Medicines used to treat mood, anxiety, psychotic or thought disorders, such as:
    - tricyclic antidepressants
    - lithium
    - SSRIs
    - SNRIs
    - antipsychotic drugs
  - Medicines used to treat pain such as:
    - tramadol
  - Medicines used to thin your blood such as:
    - warfarin
  - Medicines used to treat heartburn such as:
    - Cimetidine
  - Over-the-counter medicines or supplements such as:
    - Aspirin or other NSAIDs
    - Tryptophan
    - St. John's Wort
- have heart problems
- have diabetes
- have liver problems
- have kidney problems
- have thyroid problems
- have or had seizures or convulsions
- have bipolar disorder or mania
- have low sodium levels in your blood
- have high blood pressure
- have high cholesterol
- have or had bleeding problems
- are pregnant or plan to become pregnant. It is not known if venlafaxine hydrochloride extended-release capsules will harm your unborn baby. Talk to your healthcare provider about the benefits and risks of treating depression during pregnancy
- are breast-feeding or plan to breast-feed. Some venlafaxine hydrochloride extended-release capsules may pass into your breast milk. Talk to your healthcare provider about the best way to feed your baby while taking venlafaxine hydrochloride extended-release capsules.

Tell your healthcare provider about all the medicines that you take, including prescription and non-prescription medicines, vitamins, and herbal supplements. Venlafaxine hydrochloride extended-release capsules and some medicines may interact with each other, may not work as well, or may cause serious side effects.

Your healthcare provider or pharmacist can tell you if it is safe to take venlafaxine hydrochloride extended-release capsules with your other medicines. Do not start or stop any medicine while taking venlafaxine hydrochloride extended-release capsules without talking to your healthcare provider first.

If you take venlafaxine hydrochloride extended-release capsules, you should not take any other medicines that contain (venlafaxine) including: venlafaxine HCl.

How should I take venlafaxine hydrochloride extended-release capsules ?

- Take venlafaxine hydrochloride extended-release capsules exactly as prescribed. Your healthcare provider may need to change the dose of Venlafaxine hydrochloride extended-release capsules until it is the right dose for you.
- Venlafaxine hydrochloride extended-release capsules is to be taken with food.
- If you miss a dose of venlafaxine hydrochloride extended-release capsules, take the missed dose as soon as you remember. If it is almost time for the next dose, skip the missed dose and take your next dose at the regular time. Do not take two doses of venlafaxine hydrochloride extended-release capsules at the same time.
- If you take too much venlafaxine hydrochloride extended-release capsules, call your healthcare provider or poison control center right away, or get emergency treatment.
- When switching from another antidepressant to venlafaxine hydrochloride extended-release capsules your doctor may want to lower the dose of the initial antidepressant first to avoid side effects

What should I avoid while taking venlafaxine hydrochloride extended-release capsules ?

Venlafaxine hydrochloride extended-release capsules can cause sleepiness or may affect your ability to make decisions, think clearly, or react quickly. You should not drive, operate heavy machinery, or do other dangerous activities until you know how venlafaxine hydrochloride extended-release capsules affects you. Do not drink alcohol while using venlafaxine hydrochloride extended-release capsules.

What are the possible side effects of venlafaxine hydrochloride extended-release capsules?

Venlafaxine hydrochloride extended-release capsules may cause serious side effects, including:

- See "What is the most important information I should know about venlafaxine hydrochloride extended-release capsules?"
- Increased cholesterol- have your cholesterol checked regularly
- Newborns whose mothers take venlafaxine hydrochloride extended-release capsules in the third trimester may have problems right after birth including:
  - problems feeding and breathing
  - seizures
  - shaking, jitteriness or constant crying
  - Angle-closure glaucoma

Common possible side effects in people who take venlafaxine hydrochloride extended-release capsules include :

- unusual dreams
- sexual problems
- loss of appetite, constipation, diarrhea, nausea or vomiting, or dry mouth
- feeling tired, fatigued or overly sleepy
- change in sleep habits, problems sleeping
- yawning
- tremor or shaking
- dizziness, blurred vision
- sweating
- feeling anxious, nervous or jittery
- headache
- increase in heart rate

Tell your healthcare provider if you have any side effect that bothers you or that does not go away. These are not all the possible side effects of venlafaxine hydrochloride extended-release capsules. For more information, ask your healthcare provider or pharmacist.

CALL YOUR DOCTOR FOR MEDICAL ADVICE ABOUT SIDE EFFECTS. YOU MAY REPORT SIDE EFFECTS TO THE FDA AT 1-800-FDA-1088.

How should I store venlafaxine hydrochloride extended-release capsules?

- Store venlafaxine hydrochloride extended-release capsules at room temperature between 68°F and 77°F (20°C to 25°C).
- Keep venlafaxine hydrochloride extended-release capsules in a dry place.

Keep venlafaxine hydrochloride extended-release capsules and all medicines out of the reach of children.

General information about venlafaxine hydrochloride extended-release capsules

Medicines are sometimes prescribed for purposes other than those listed in a Medication Guide. Do not use venlafaxine hydrochloride extended-release capsules for a condition for which it was not prescribed. Do not give venlafaxine hydrochloride extended-release capsules to other people, even if they have the same condition. It may harm them.

This Medication Guide summarizes the most important information about venlafaxine hydrochloride extended-release capsules. If you would like more information, talk with your healthcare provider. You may ask your healthcare provider or pharmacist for information about venlafaxine hydrochloride extended-release capsules that is written for healthcare professionals.

What are the ingredients in venlafaxine hydrochloride extended-release capsules?

Active ingredient: (venlafaxine)

Inactive ingredients:

- Extended-Release Capsules: cellulose, ethylcellulose, gelatin, hypromellose, iron oxides, and titanium dioxide.

This Medication Guide has been approved by the U.S. Food and Drug Administration for all antidepressants.

This product's label may have been updated. For current full prescribing information, please visit www.pfizer.com

Distributed by:
Apotex Corp.
Weston, Florida 33326

LAB-0544-4.0
May 2014